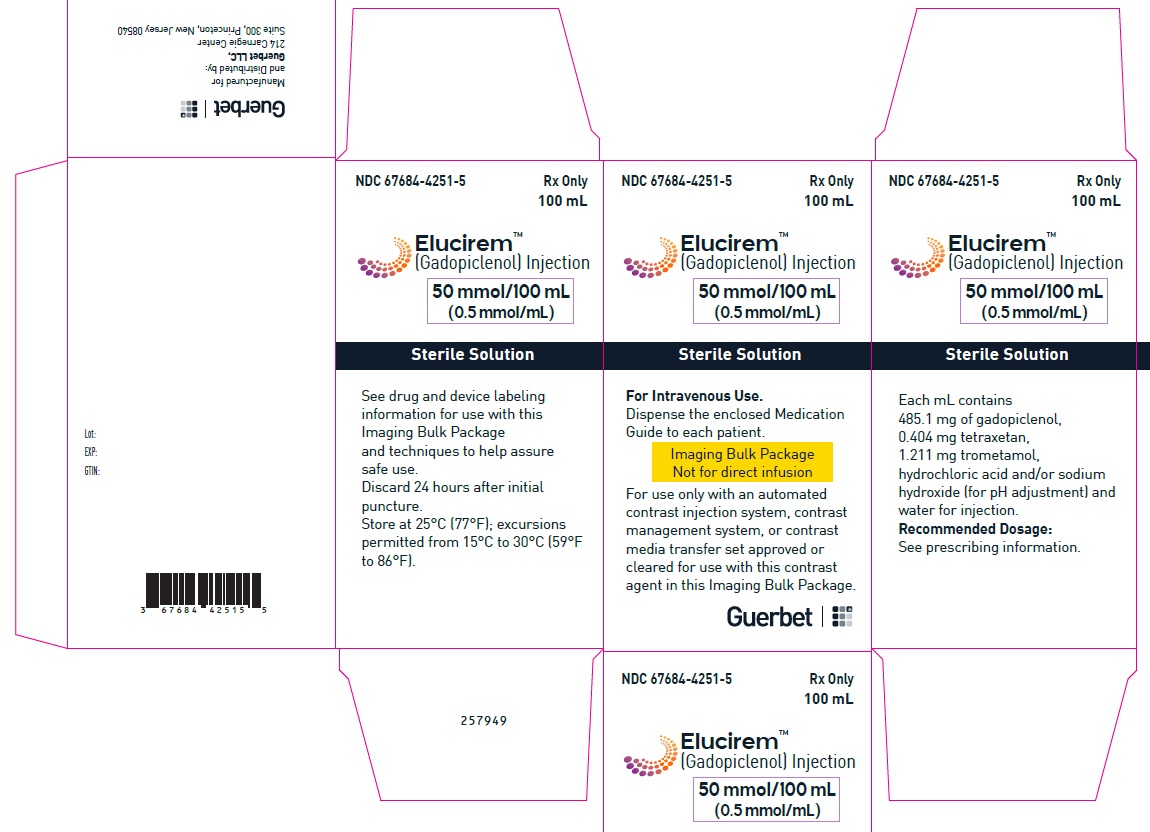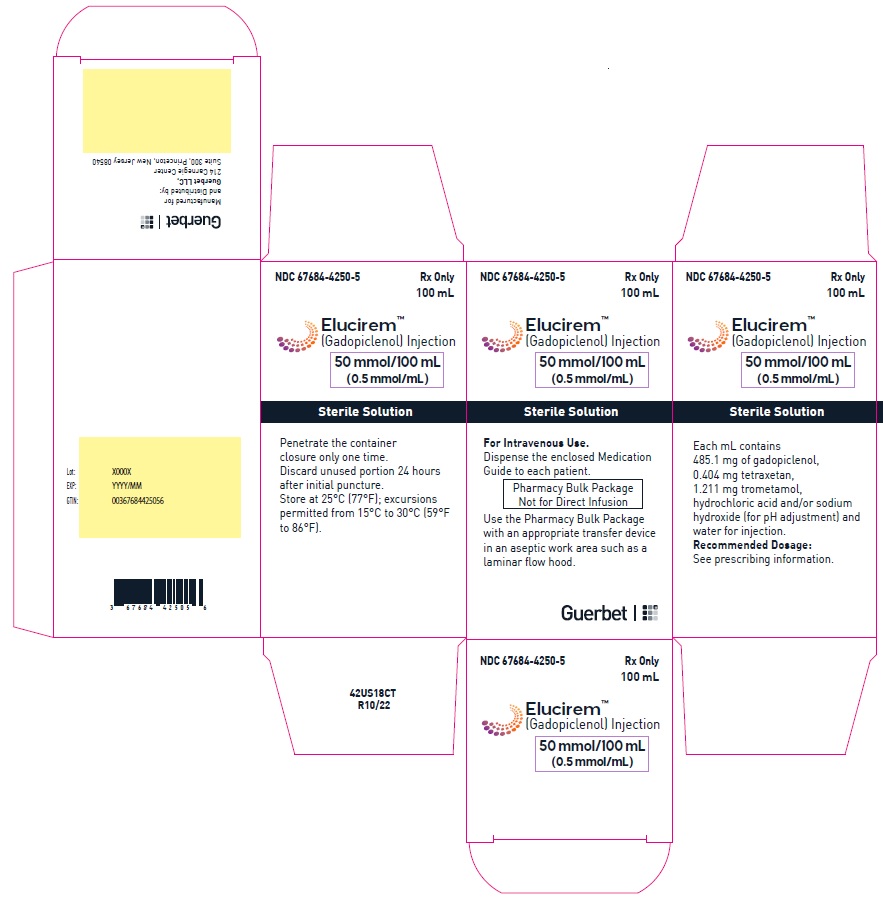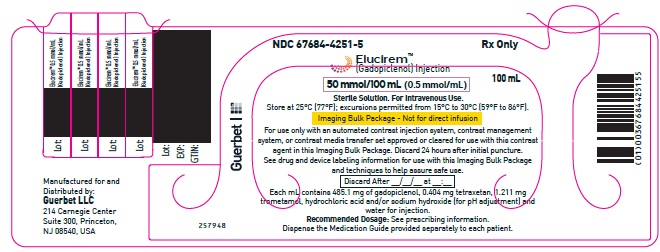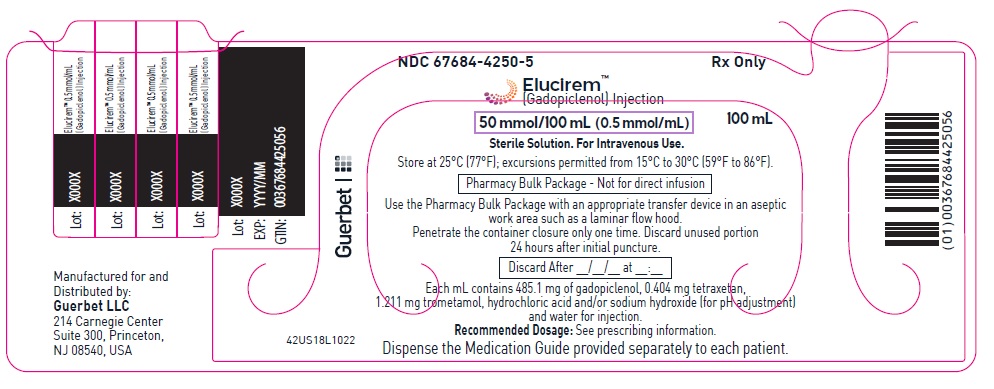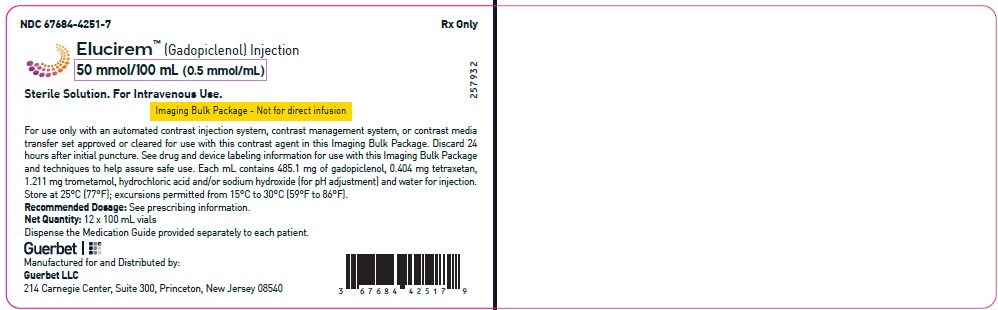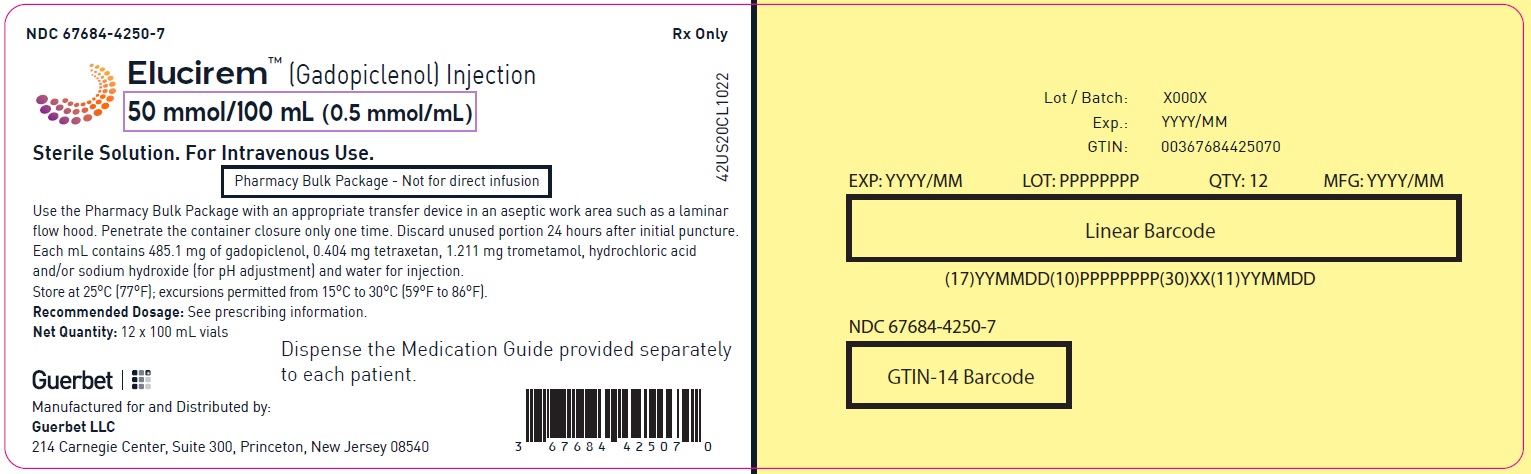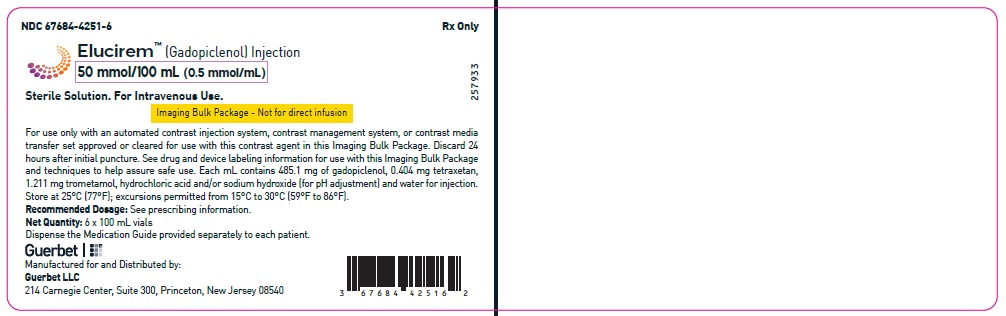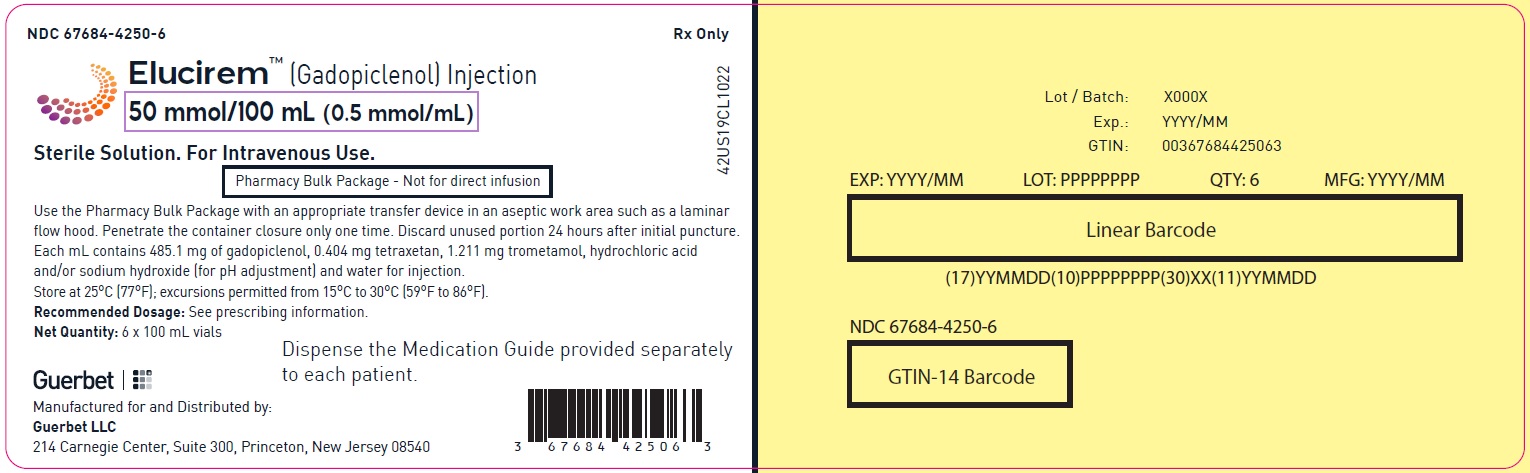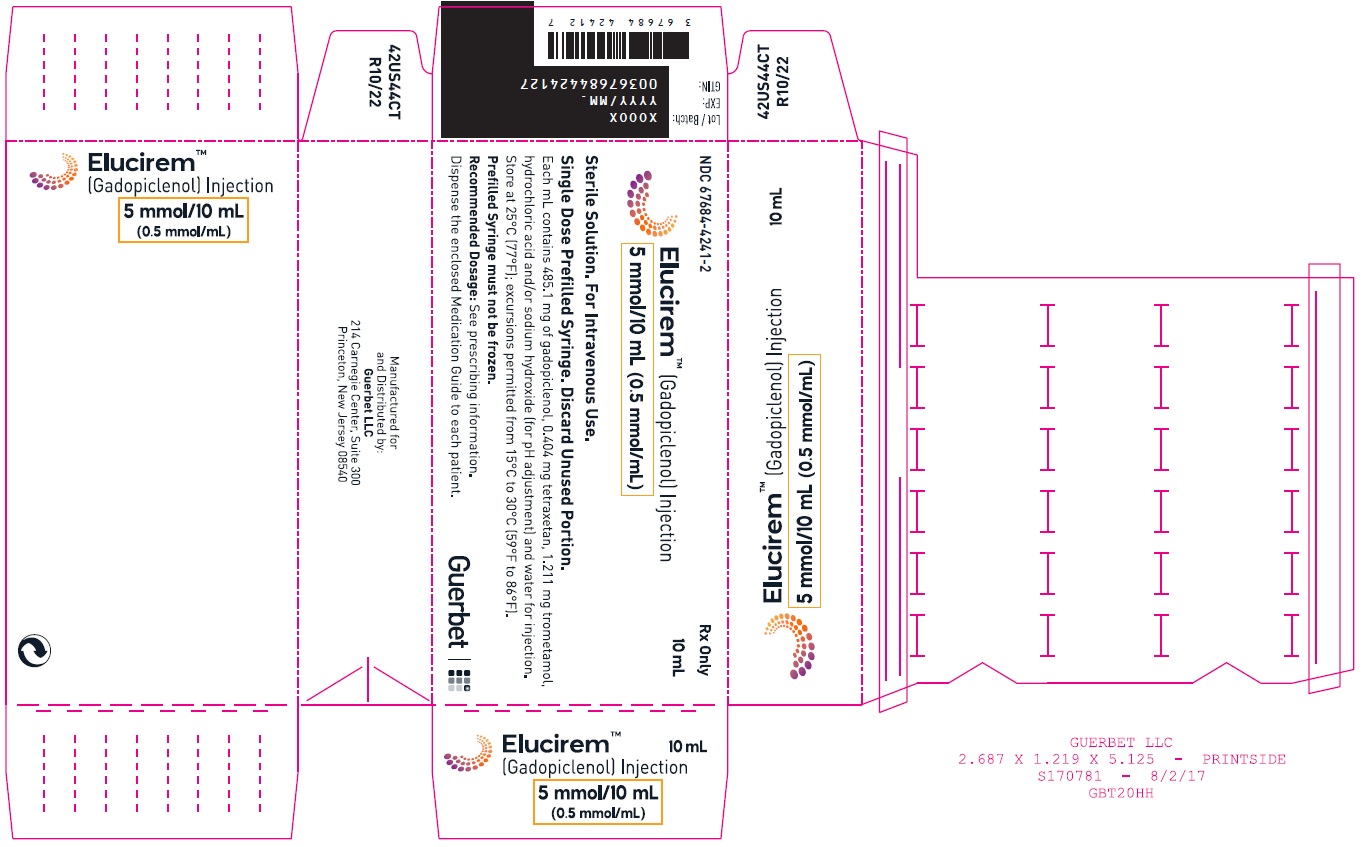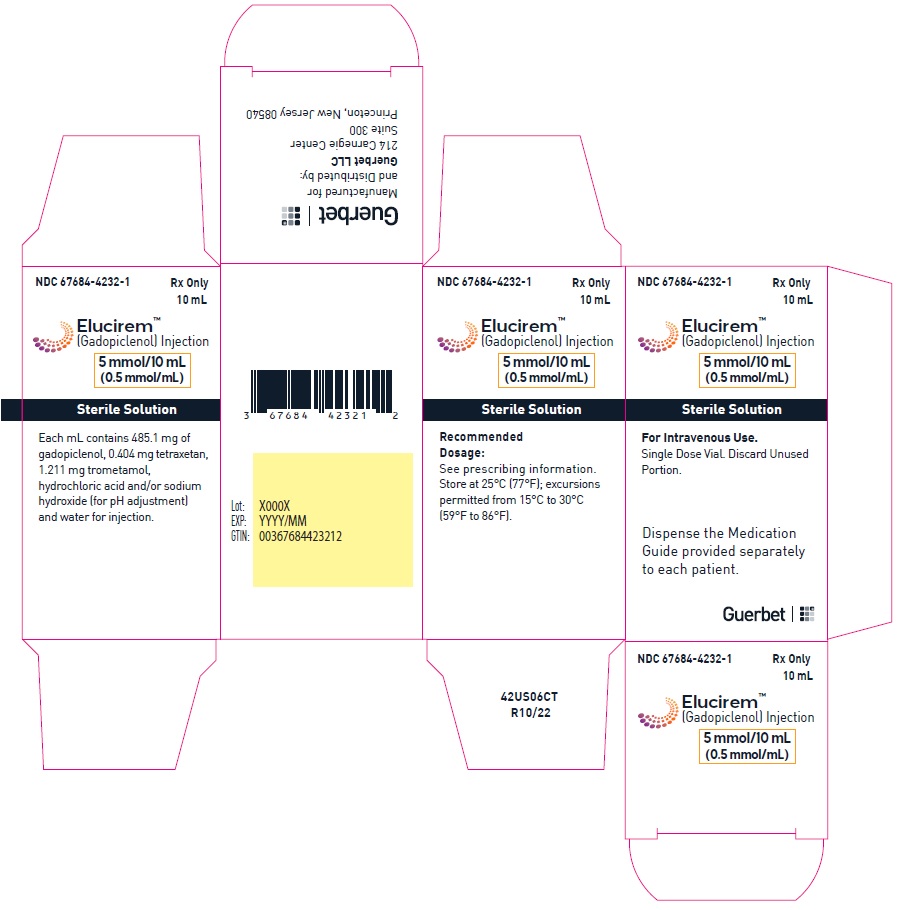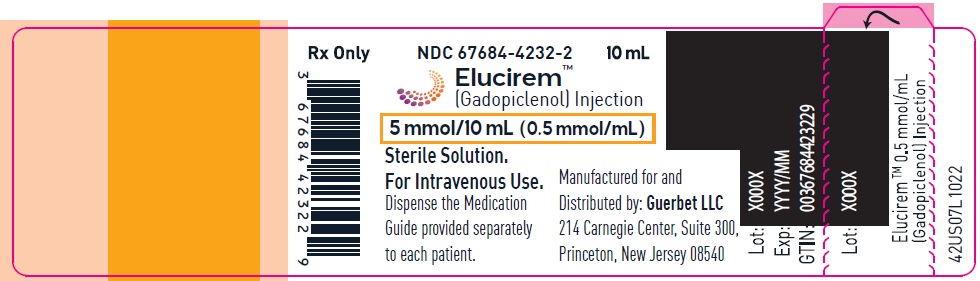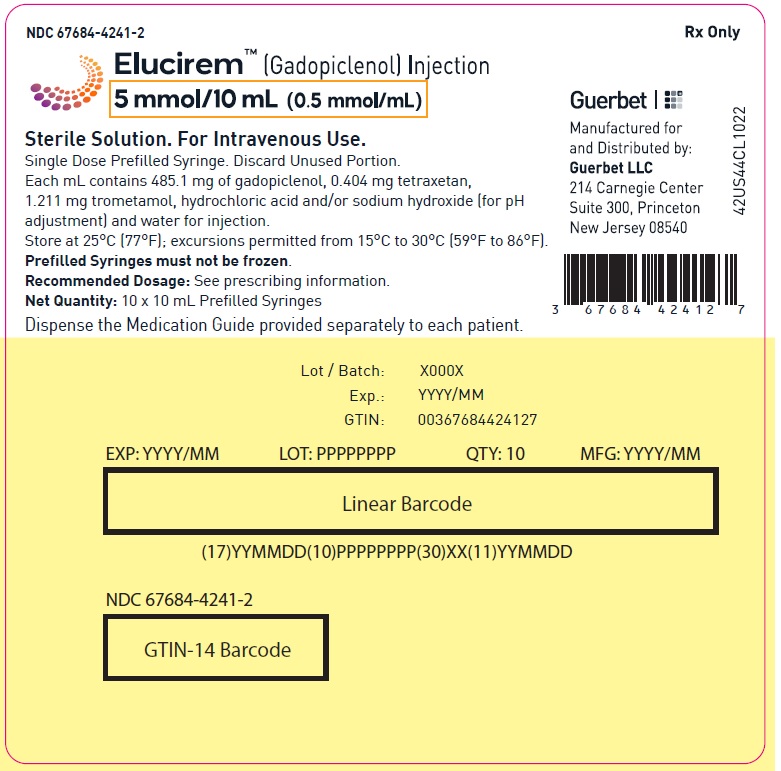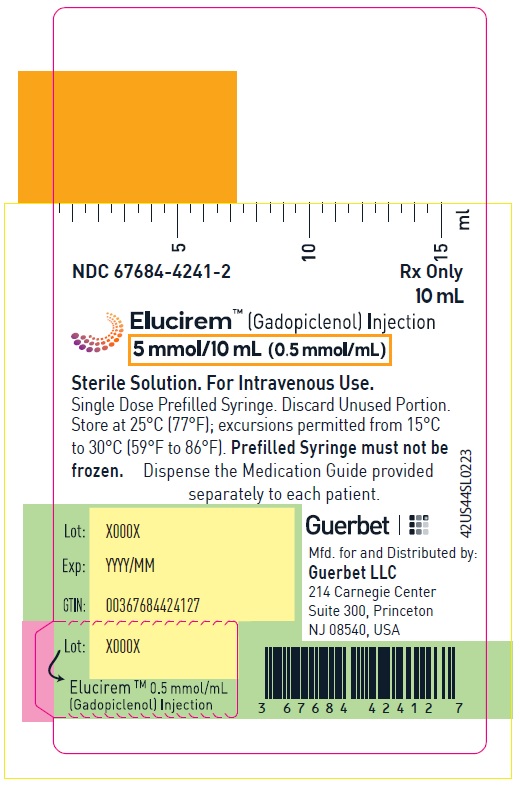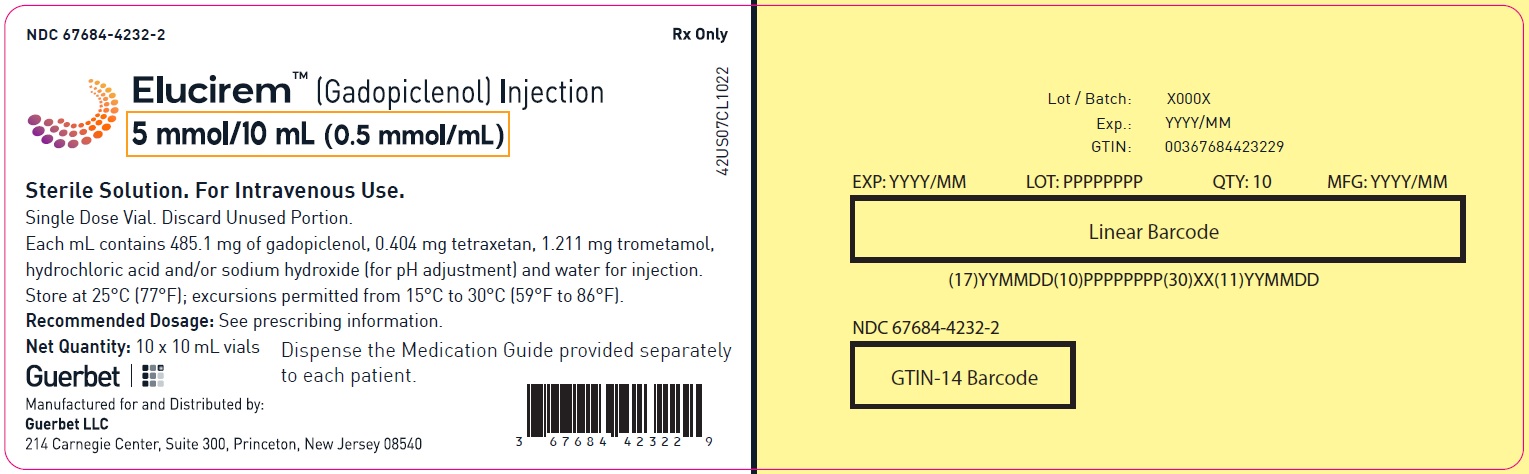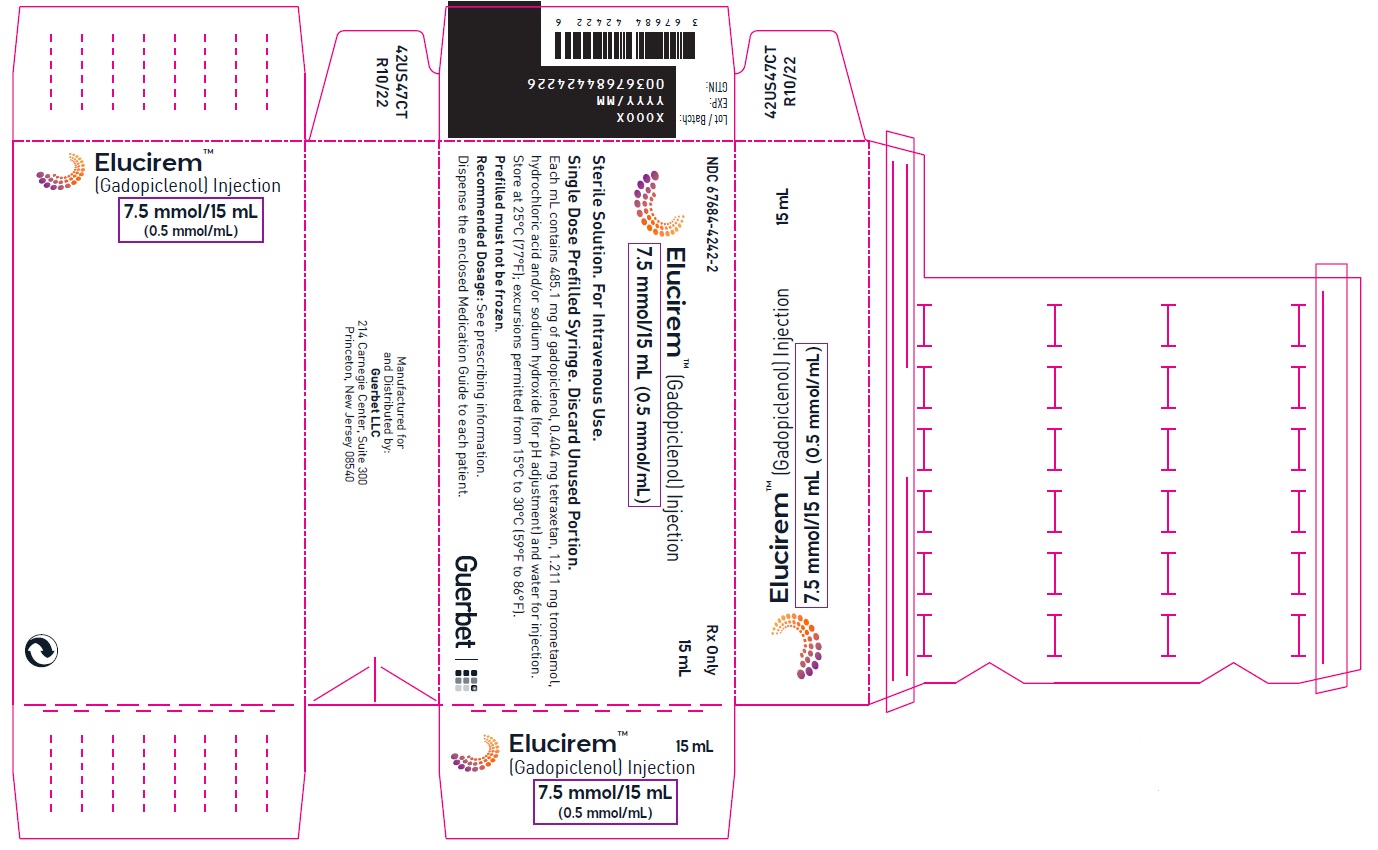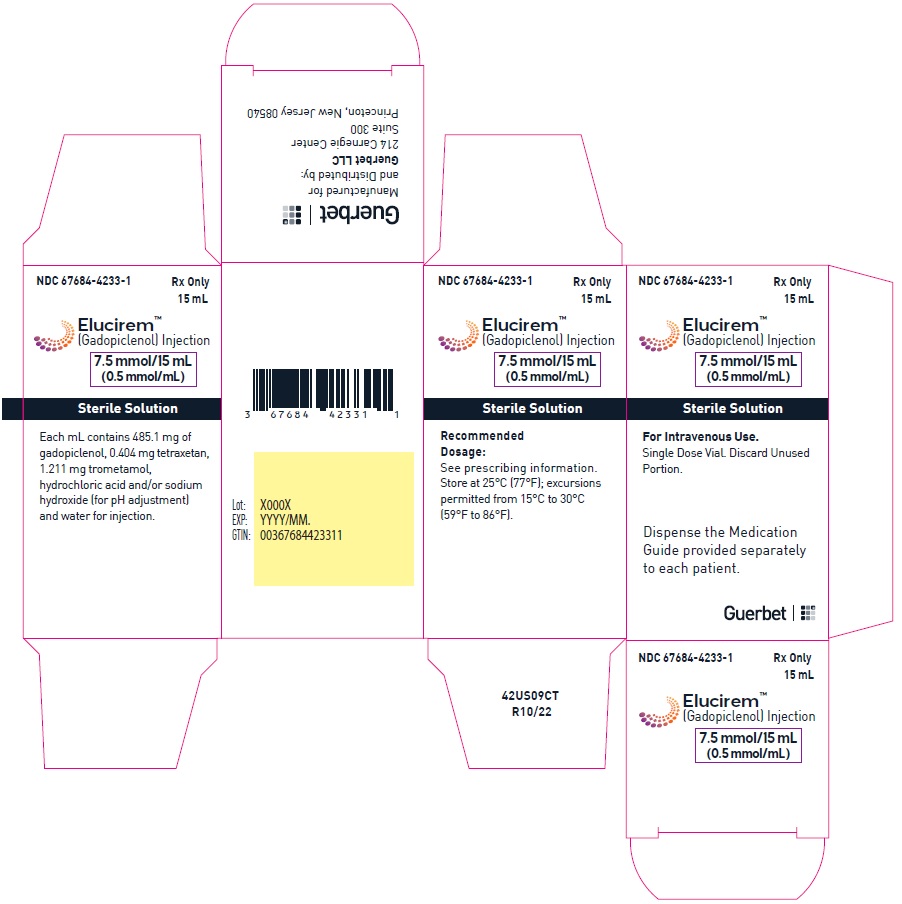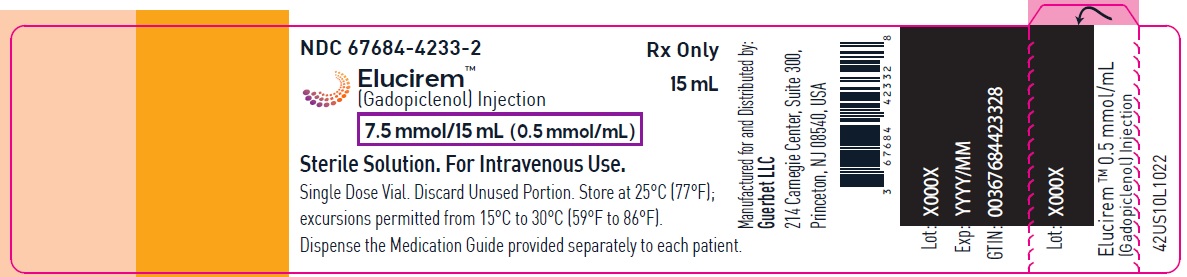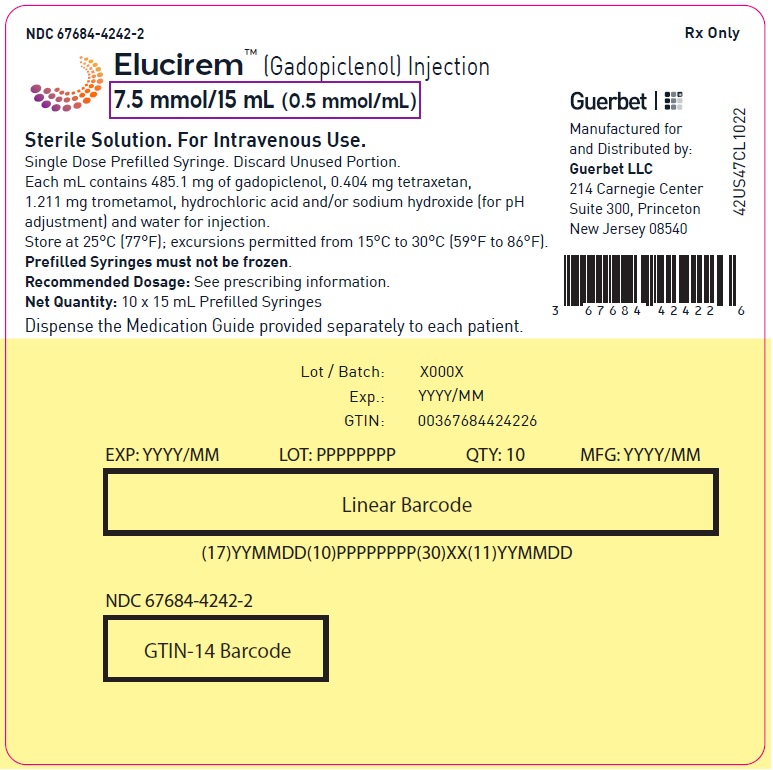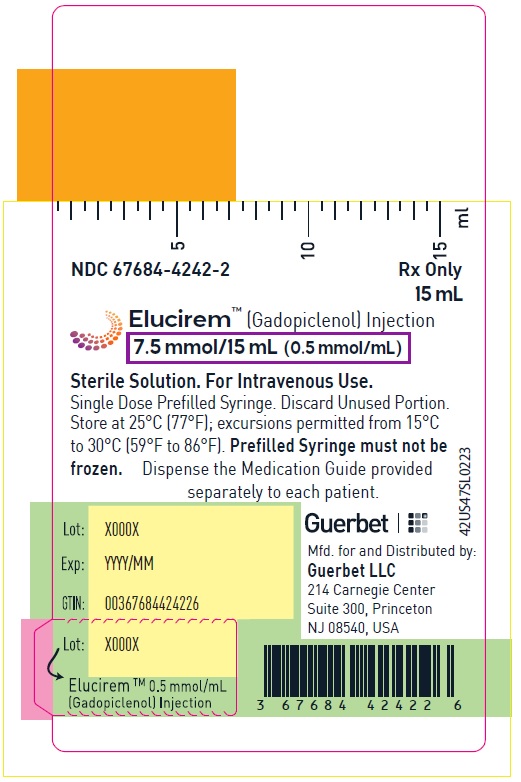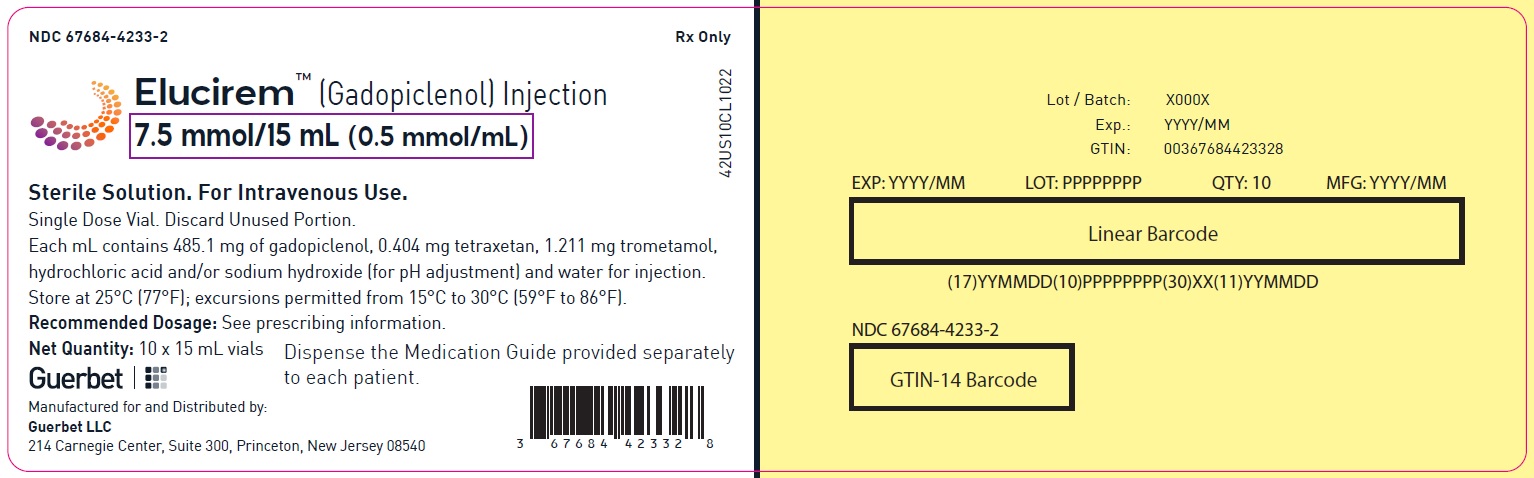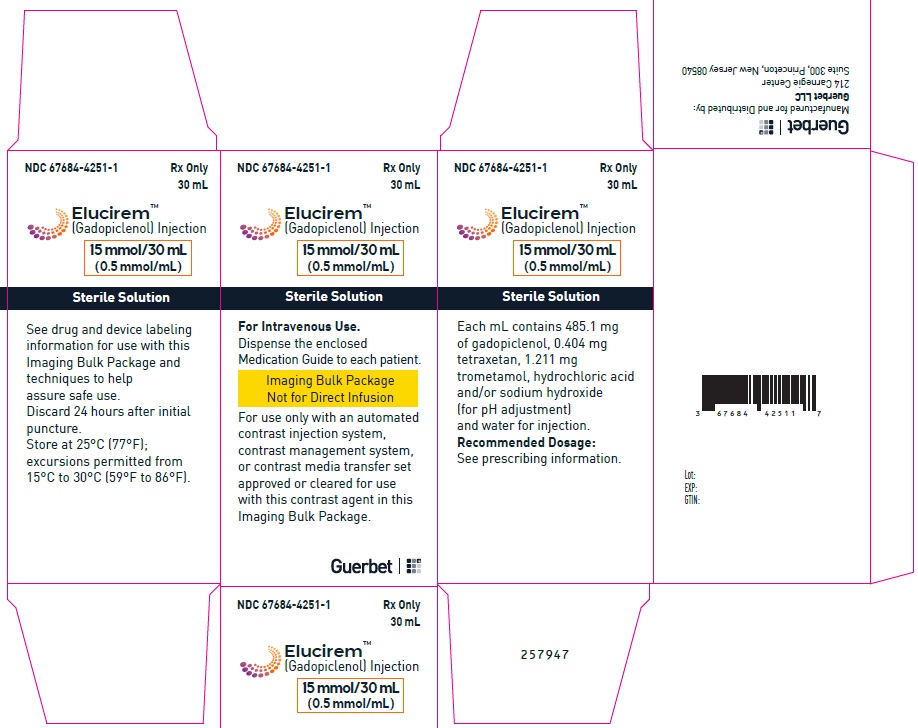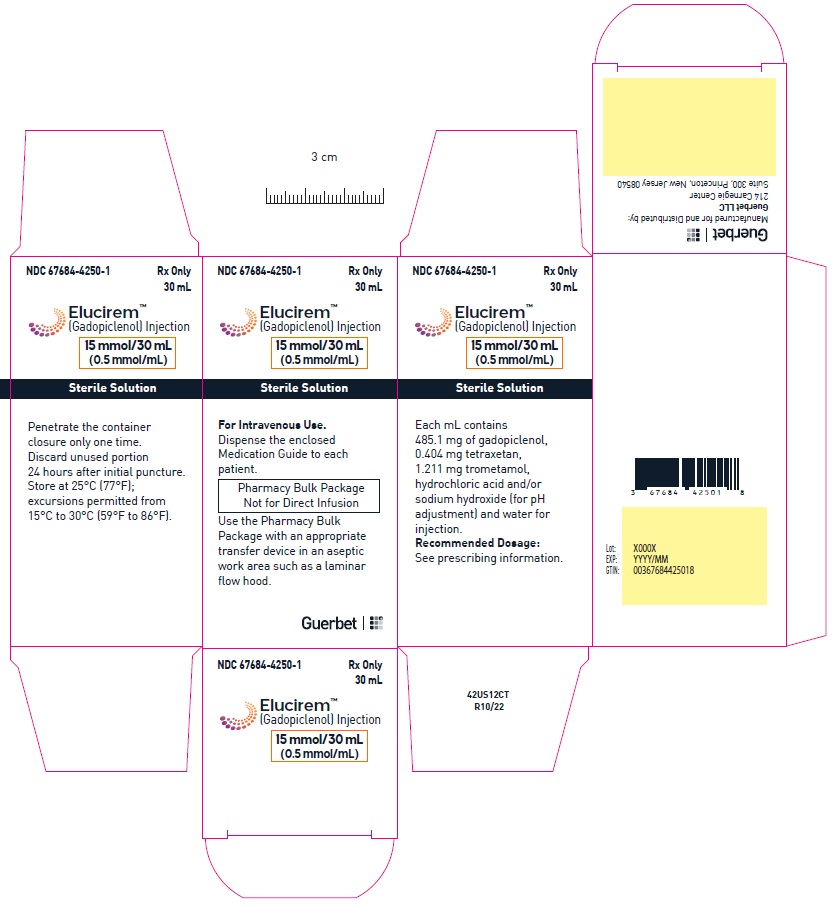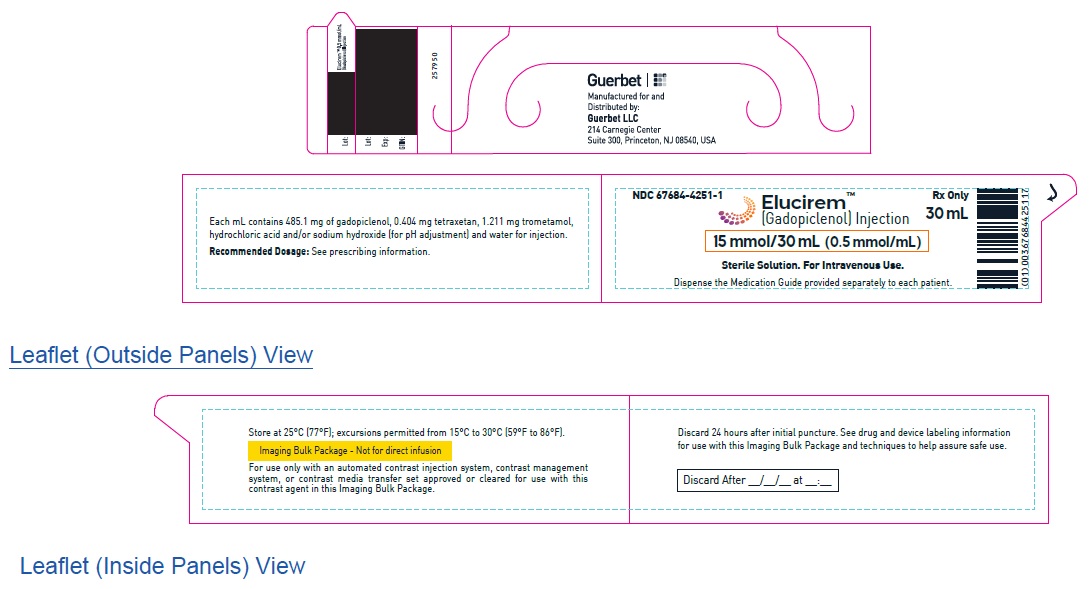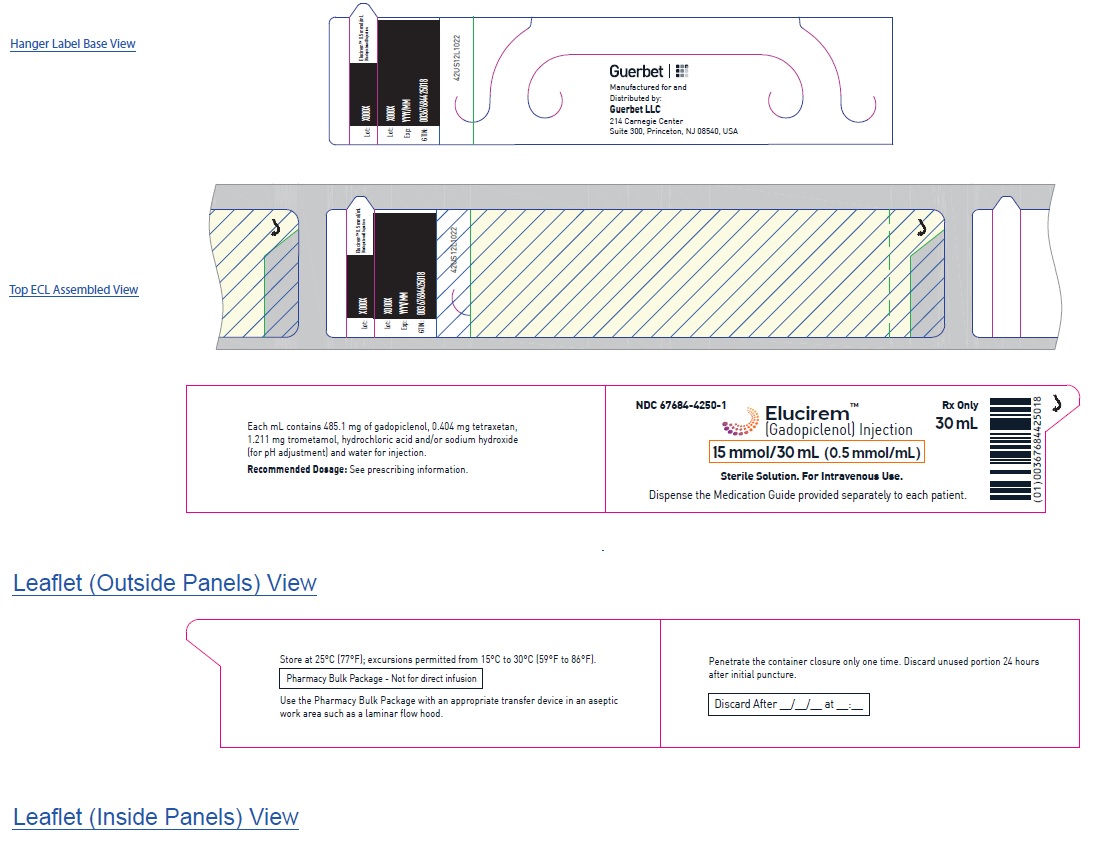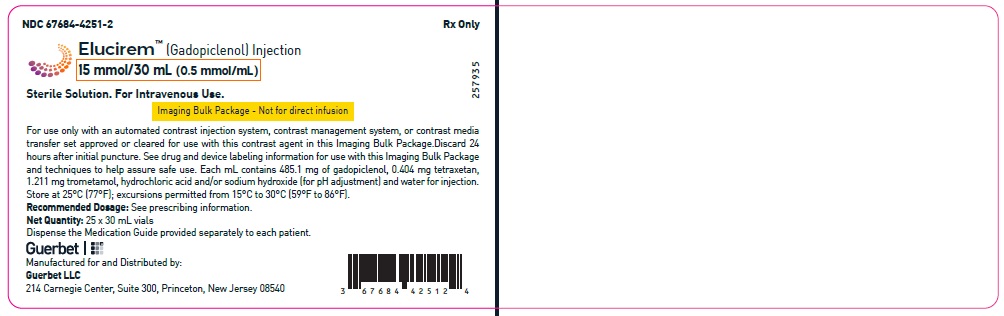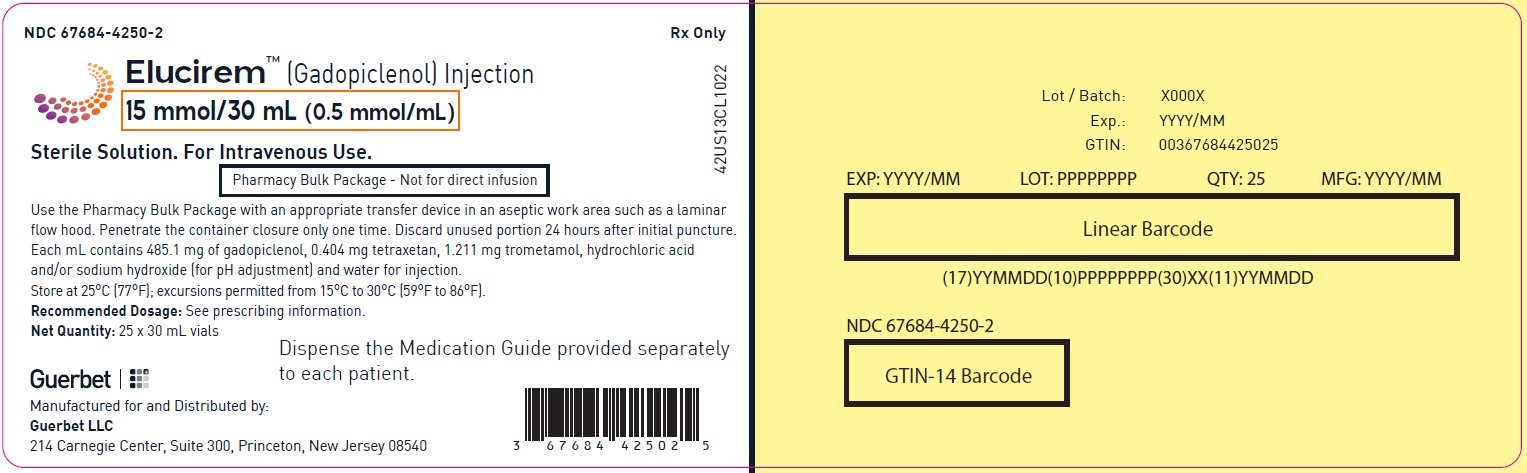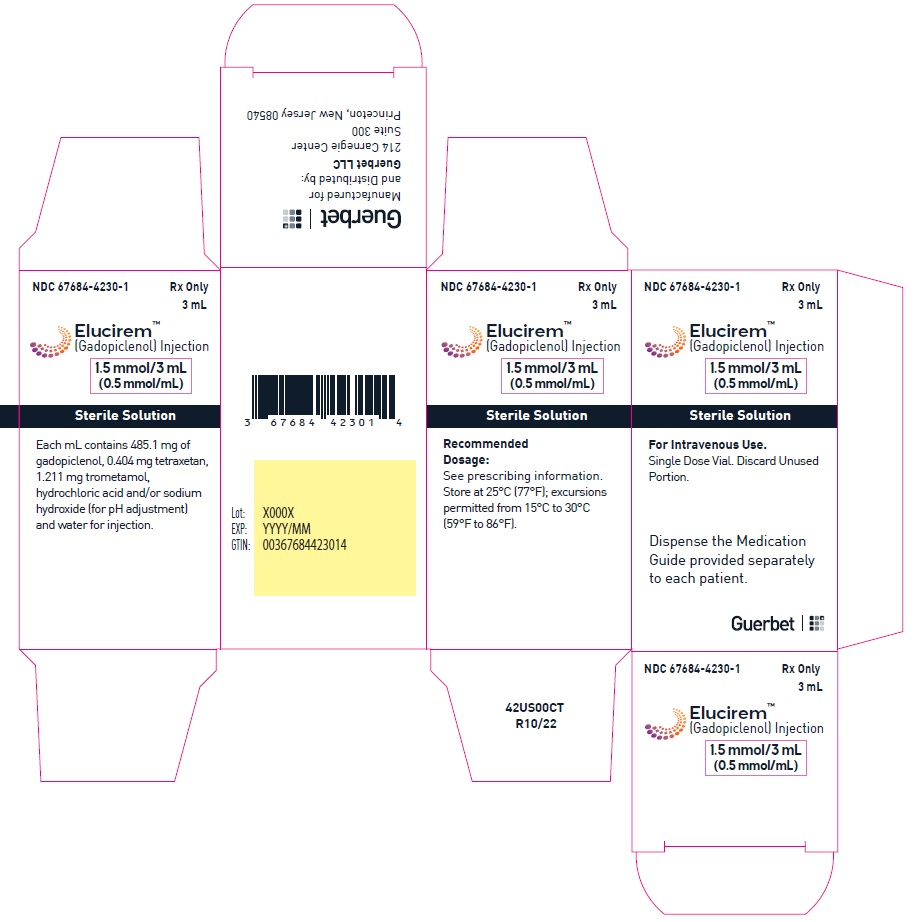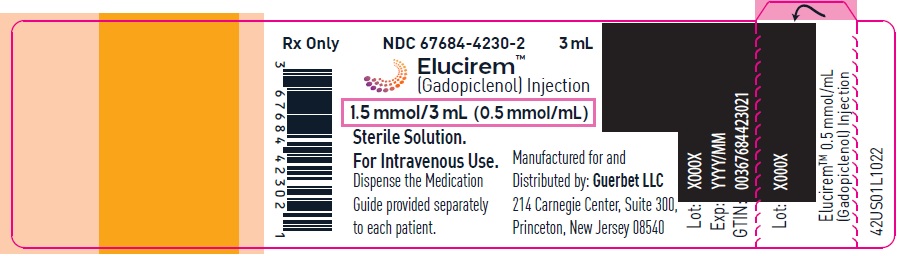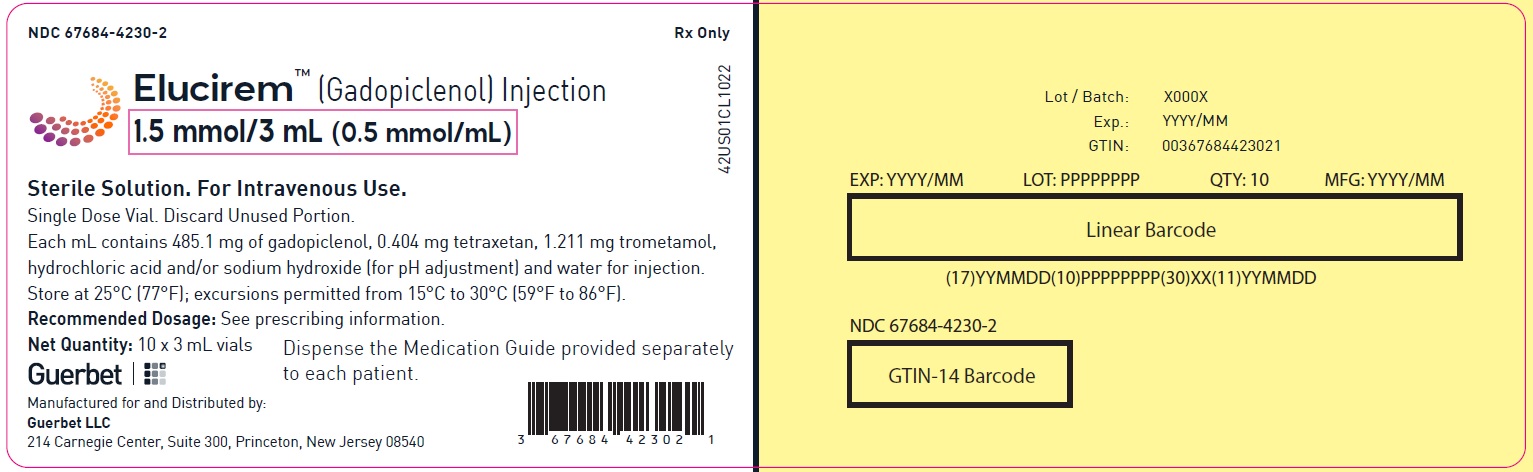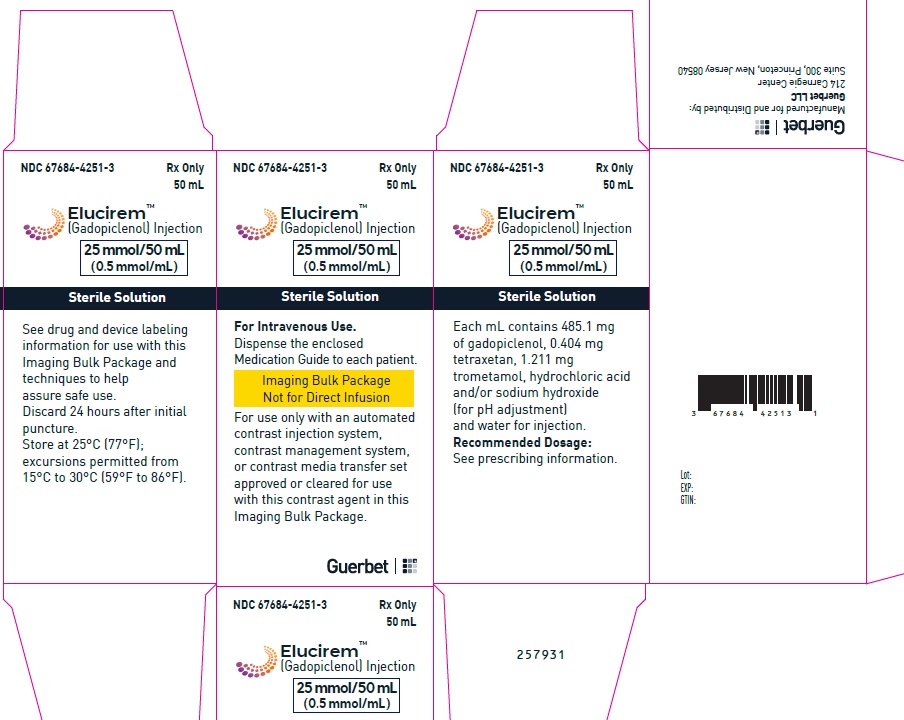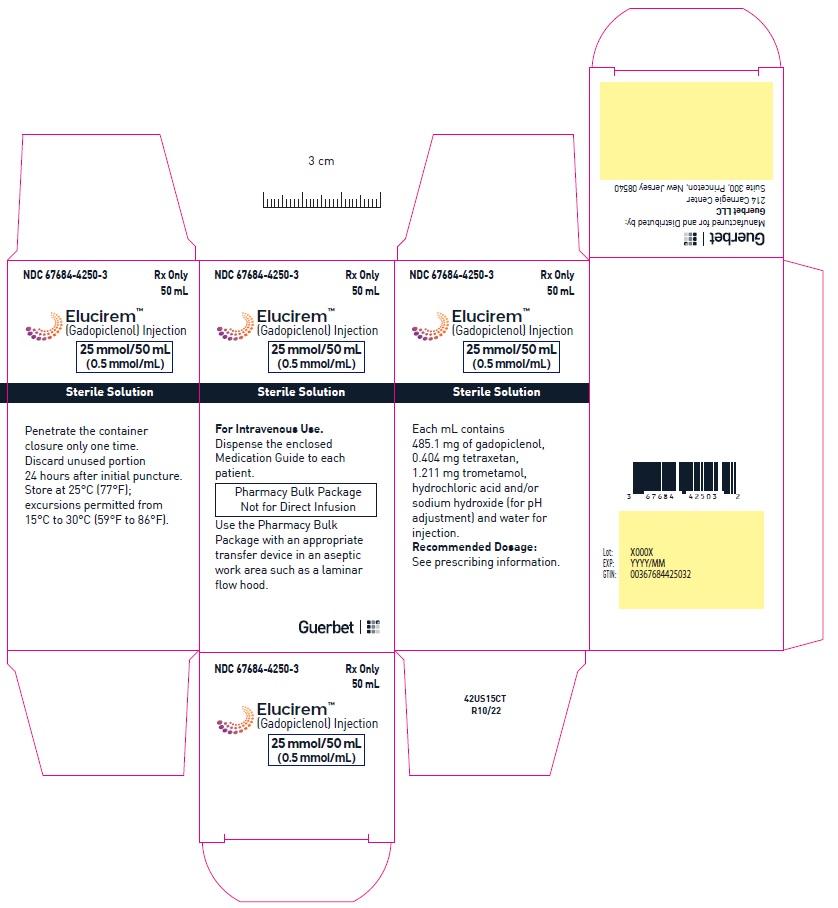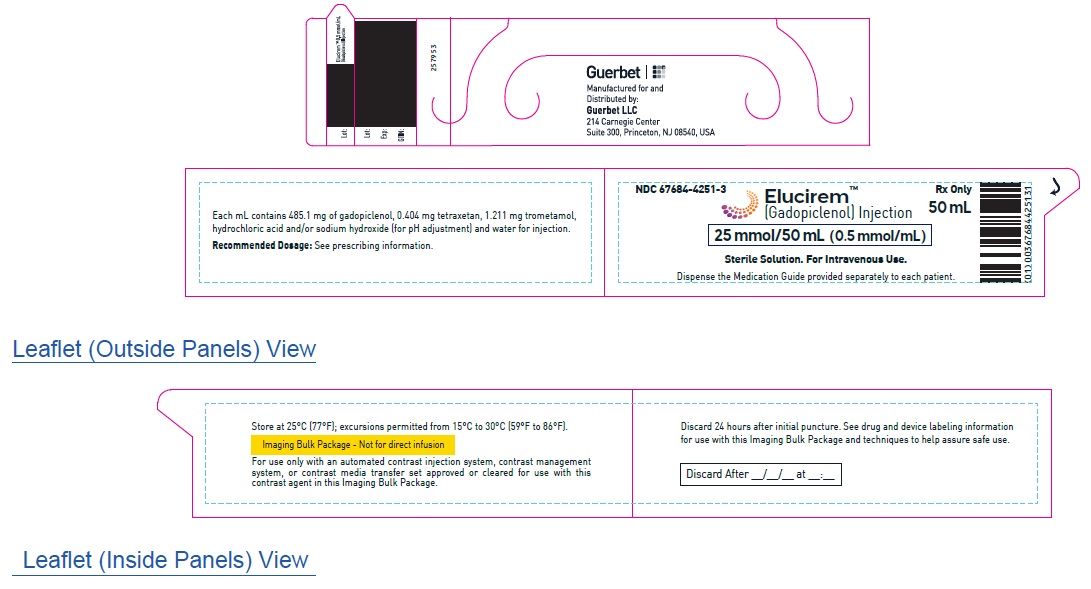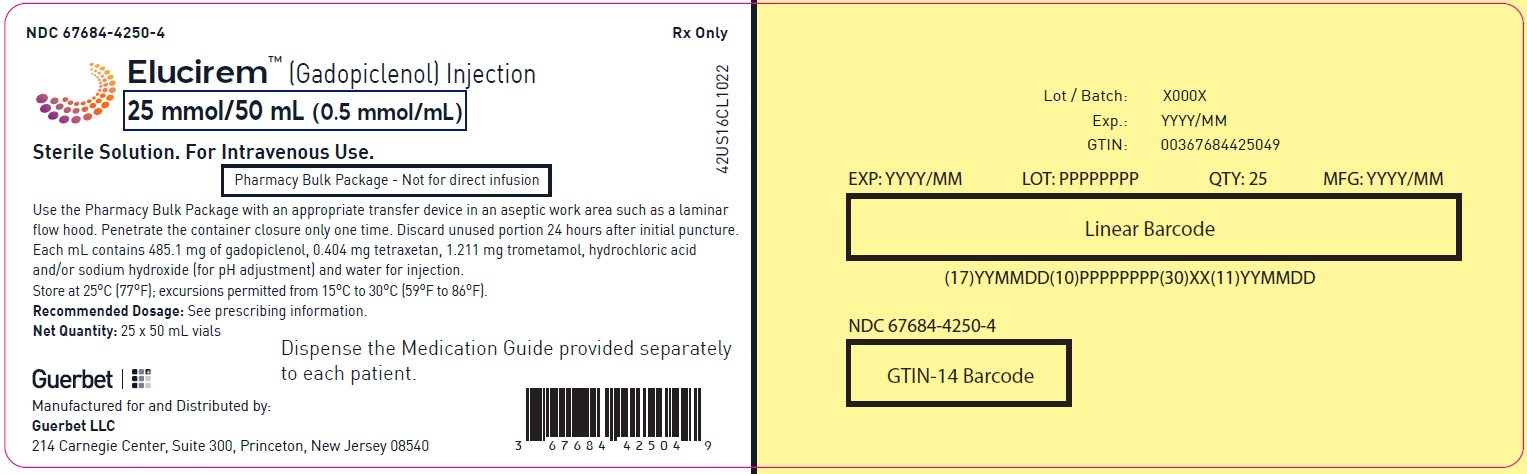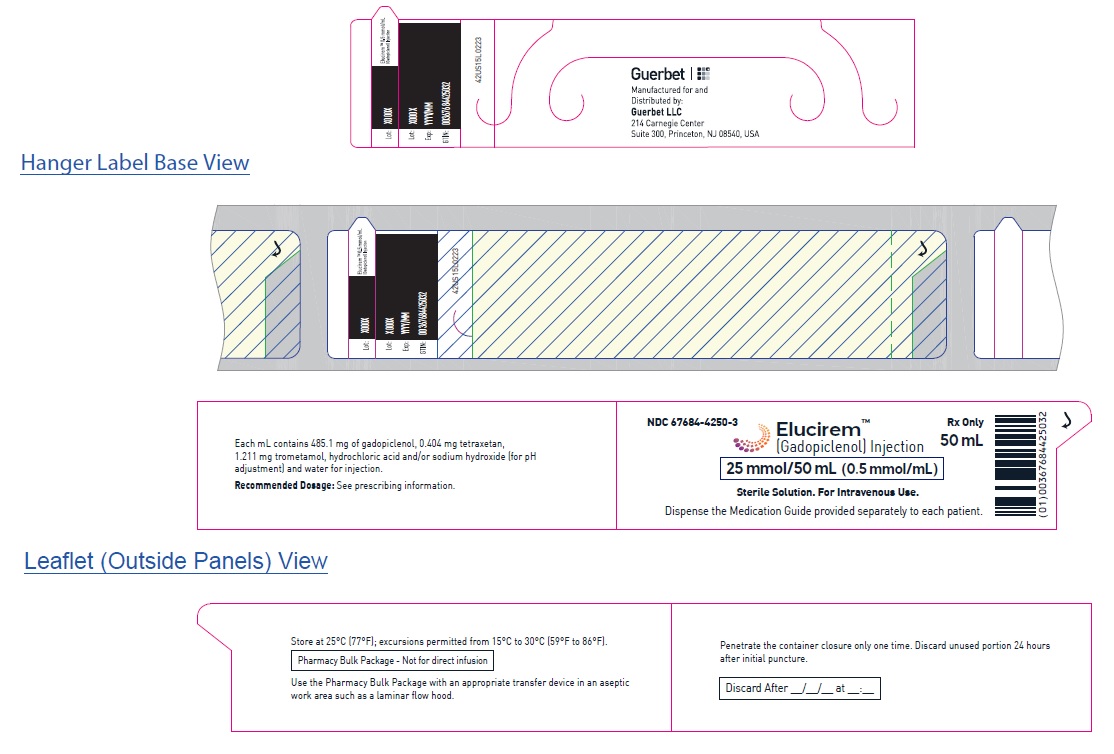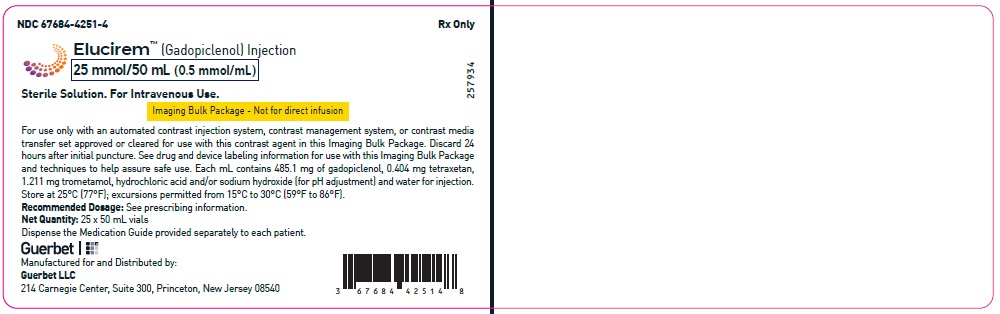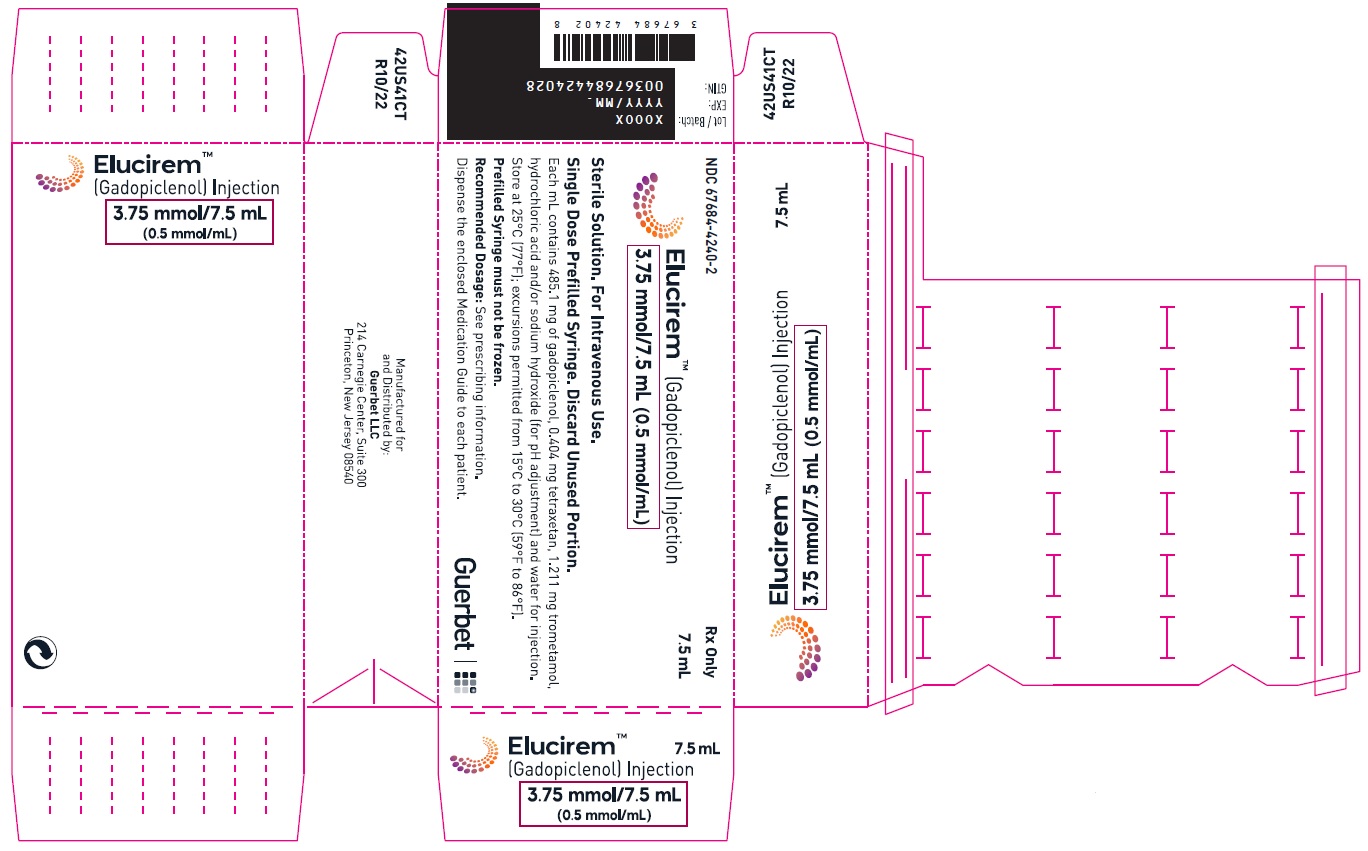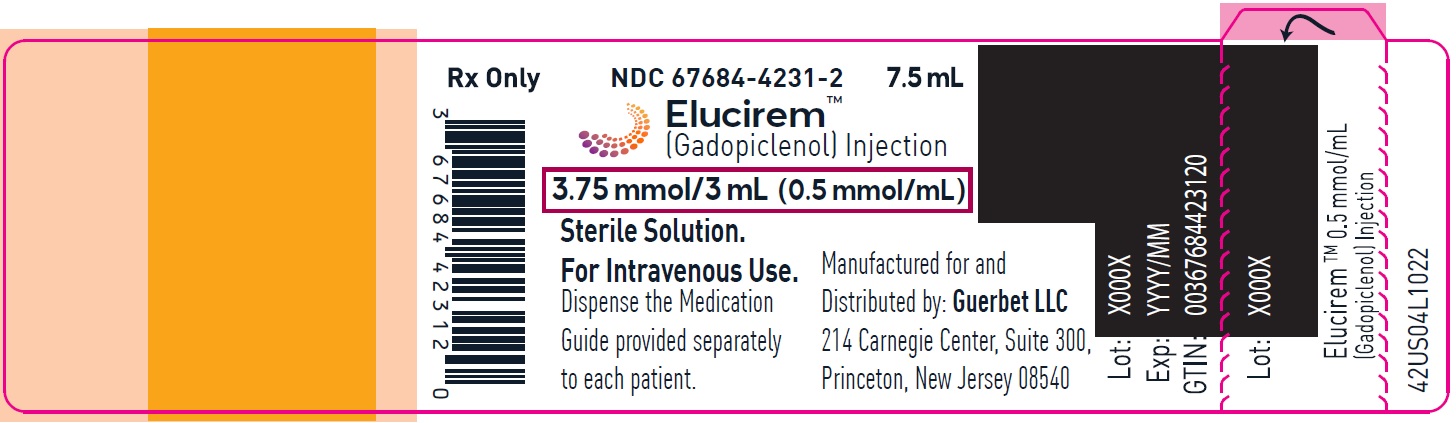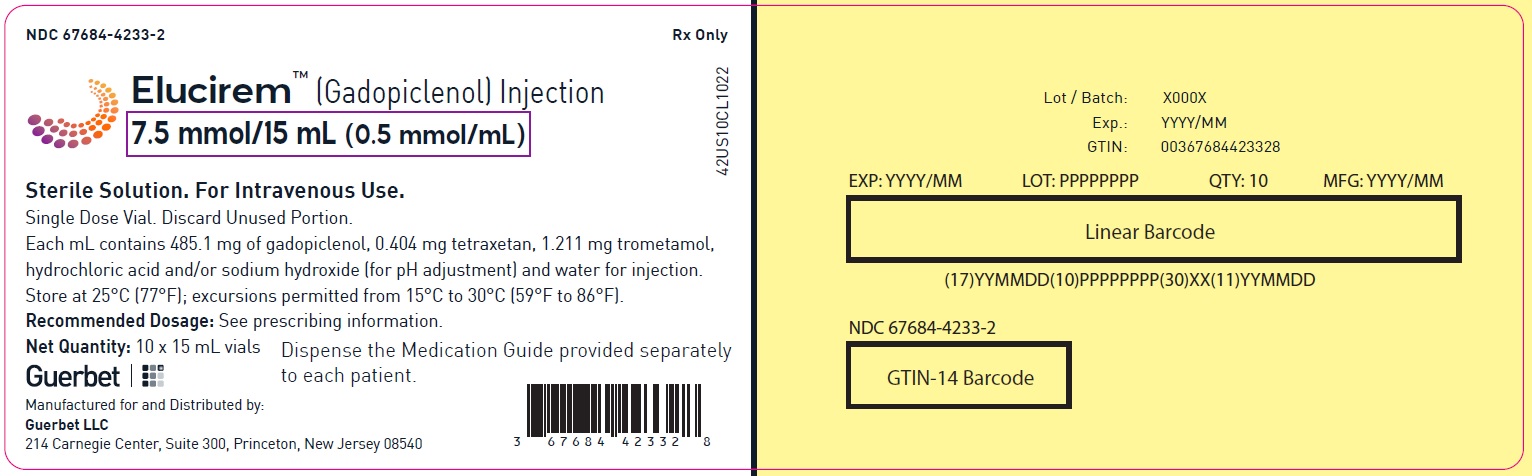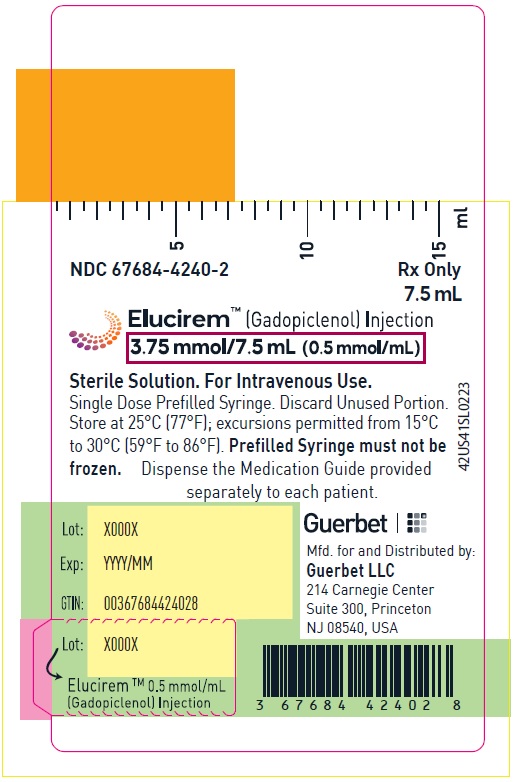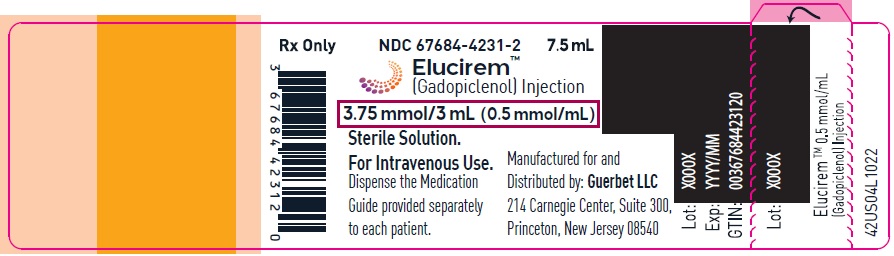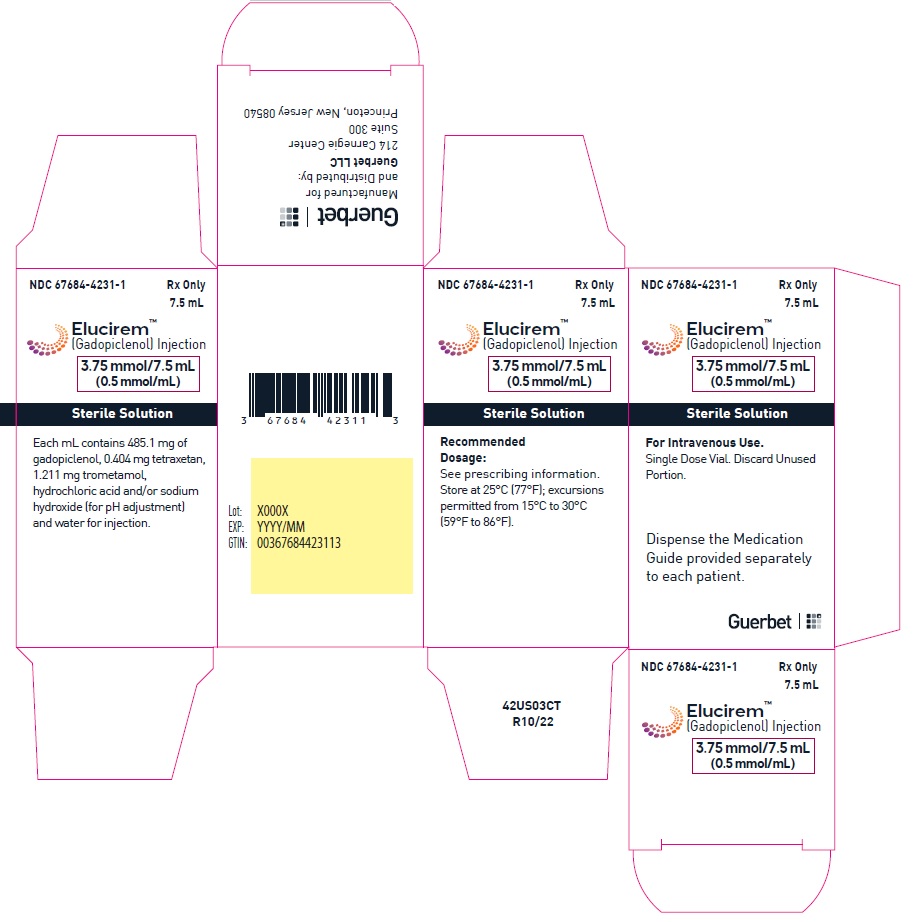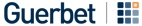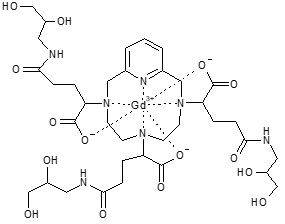 DRUG LABEL: ELUCIREM
NDC: 67684-4230 | Form: INJECTION
Manufacturer: Guerbet LLC
Category: prescription | Type: HUMAN PRESCRIPTION DRUG LABEL
Date: 20251212

ACTIVE INGREDIENTS: Gadopiclenol 485.1 mg/1 mL
INACTIVE INGREDIENTS: Tetraxetan; Sodium hydroxide; hydrochloric acid; Tromethamine; WATER

HIGHLIGHTS OF PRESCRIBING INFORMATION

These highlights do not include all the information needed to use ELUCIREMTM safely and effectively. See full prescribing information for ELUCIREM.
ELUCIREMTM (gadopiclenol) injection, for intravenous use
Initial U.S. Approval: 2022

RECENT MAJOR CHANGES

Dosage and Administration
Directions for Use of Imaging Bulk Package (2.5) 11/2025

WARNING: RISK ASSOCIATED WITH INTRATHECAL USE and NEPHROGENIC SYSTEMIC FIBROSIS

See full prescribing information for complete boxed warning

- Intrathecal administration of gadolinium-based contrast agents (GBCAs) can cause serious adverse reactions including death, coma, encephalopathy, and seizures. ELUCIREM is not approved for intrathecal use. (5.1)

- GBCAs increase the risk for nephrogenic systemic fibrosis (NSF) among patients with impaired elimination of the drugs. Avoid use of ELUCIREM in these patients unless the diagnostic information is essential and not available with non-contrasted MRI or other modalities. The risk for NSF appears highest among patients with:
  - Chronic, severe kidney disease (GFR <30 mL/min/1.73 m^2), or
  - Acute kidney injury.

Screen patients for acute kidney injury and other conditions that may reduce renal function. For patients at risk for chronically reduced renal function (for example, age >60 years, hypertension or diabetes), estimate the glomerular filtration rate (GFR) through laboratory testing. (5.2)

1 INDICATIONS AND USAGE

ELUCIREM is a gadolinium-based contrast agent indicated in adult and pediatric patients aged 2 years and older for use with magnetic resonance imaging (MRI) to detect and visualize lesions with abnormal vascularity in:

- the central nervous system (brain, spine, and associated tissues),
- the body (head and neck, thorax, abdomen, pelvis, and musculoskeletal system). (1)

2 DOSAGE AND ADMINISTRATION

- The recommended dose for adult and pediatric patients aged 2 years and older is 0.05 mmol/kg actual body weight (equivalent to 0.1 mL/kg) administered intravenously at approximately 2 mL/sec. (2.1)

3 DOSAGE FORMS AND STRENGTHS

Injection: 0.5 mmol/mL of gadopiclenol in single-dose vials, single-dose prefilled syringes, pharmacy bulk packages, and imaging packages (3)

4 CONTRAINDICATIONS

History of hypersensitivity reactions to ELUCIREM (4)

5 WARNINGS AND PRECAUTIONS

- Hypersensitivity Reactions: Serious hypersensitivity reactions have occurred with GBCAs. Monitor patients closely for need of emergency cardiorespiratory support. (5.3)
- Gadolinium Retention: Gadolinium is retained for months or years in brain, bone, and other organs. (5.4)

6 ADVERSE REACTIONS

Most common adverse reactions (incidence >0.2%) in patients who received ELUCIREM are injection site pain, headache, nausea, injection site warmth and coldness, dizziness, and localized swelling. (6.1)

To report SUSPECTED ADVERSE REACTIONS contact GUERBET LLC at 1-877-729-6679 or FDA at 1-800-FDA-1088 or www.fda.gov/medwatch.

8 USE IN SPECIFIC POPULATIONS

Pregnancy: Use only if imaging is essential during pregnancy and cannot be delayed. (8.1)

FULL PRESCRIBING INFORMATION

WARNING: RISK ASSOCIATED WITH INTRATHECAL USE and NEPHROGENIC SYSTEMIC FIBROSIS

Risk Associated with Intrathecal Use
Intrathecal administration of gadolinium-based contrast agents (GBCAs) can cause serious adverse reactions including death, coma, encephalopathy, and seizures. ELUCIREM is not approved for intrathecal use [see Warnings and Precautions (5.1)].

Nephrogenic Systemic Fibrosis
GBCAs increase the risk for nephrogenic systemic fibrosis (NSF) among patients with impaired elimination of the drugs. Avoid use of ELUCIREM in these patients unless the diagnostic information is essential and not available with non-contrasted MRI or other modalities. NSF may result in fatal or debilitating fibrosis affecting the skin, muscle and internal organs.
The risk for NSF appears highest among patients with:

- Chronic, severe kidney disease (GFR < 30 mL/min/1.73 m^2), or
- Acute kidney injury.

Screen patients for acute kidney injury and other conditions that may reduce renal function. For patients at risk for chronically reduced renal function (e.g. age > 60 years, hypertension, diabetes), estimate the glomerular filtration rate (GFR) through laboratory testing.

For patients at highest risk for NSF, do not exceed the recommended ELUCIREM dose and allow a sufficient period of time for elimination of the drug from the body prior to any re-administration [see Warnings and Precautions (5.2)].

1 INDICATIONS AND USAGE

ELUCIREMTM is indicated in adult and pediatric patients aged 2 years and older for use with magnetic resonance imaging (MRI) to detect and visualize lesions with abnormal vascularity in:

- the central nervous system (brain, spine, and associated tissues),
- the body (head and neck, thorax, abdomen, pelvis, and musculoskeletal system).

2 DOSAGE AND ADMINISTRATION

2.1 Recommended Dosage

The recommended dose of ELUCIREM for adult and pediatric patients aged 2 years and older is 0.05 mmol/kg actual body weight (equivalent to 0.1 mL/kg) administered intravenously at approximately 2 mL/sec.

2.2 Administration and Imaging Instructions

- Use aseptic technique for all handling and administration of ELUCIREM.
- Visually inspect ELUCIREM for particulate matter and discoloration prior to administration. Do not use the solution if any particulate matter is present or the solution is discolored.
- Do not mix with other medications because of the potential for chemical incompatibility.
- Prime intravenous line before use.
- Administer ELUCIREM as an intravenous bolus injection, manually or by compatible power injector. The recommended injection rate is approximately 2 mL/second.
- Flush the intravenous line with 0.9% Sodium Chloride Injection, USP after the administration of ELUCIREM.
- Contrast MRI can begin immediately following the injection of ELUCIREM.

2.3 Directions for Use of Single-Dose Vial and Pre-filled Syringe

Vial

- Do not pierce the rubber stopper more than once.
- Aseptically draw up ELUCIREM into a disposable syringe and use immediately.
- If solidification occurs in the vial because of exposure to the cold, bring the vial of ELUCIREM to room temperature before use and inspect that the solution is clear, colorless to yellow without any particulate matter and discoloration.
- Discard any unused portion.

Pre-filled syringe

- Remove the tip cap of the syringe, screw the plunger rod and use immediately.
- All luer connections should be gently hand tightened without over tightening, to ensure secure connections and to prevent damage to the device.
- Pre-filled syringes must not be frozen. Frozen pre-filled syringes of ELUCIREM should be discarded.
- Discard any unused portion.

2.4 Directions for Use of Pharmacy Bulk Package

- Do not use the Pharmacy Bulk Package for direct infusion.
- Perform the transfer of ELUCIREM from the Pharmacy Bulk Package in an aseptic work area, such as laminar flow hood, using aseptic technique and suitable transfer device for filling empty syringes.
- Penetrate the closure only one time. Once the container closure is punctured, do not remove the Pharmacy Bulk Package from the aseptic work area.
- The Pharmacy Bulk Package is used with an appropriate transfer device for filling empty sterile syringes. Use each individual dose of ELUCIREM promptly following withdrawal from the Pharmacy Bulk Package.
- Use the contents of the Pharmacy Bulk Package within 24 hours at room temperature after initial puncture.
- If solidification occurs in the vial because of exposure to the cold, bring the vial of ELUCIREM to room temperature before use and inspect that the solution is clear, colorless to yellow without any particulate matter and discoloration.

2.5 Directions for Use of Imaging Bulk Package

- ELUCIREM Imaging Bulk Package (IBP) is for intravenous use and not for direct infusion.
- The IBP is a container of a sterile preparation for parenteral use that contains multiple single doses of ELUCIREM for multiple patients for use with an automated contrast injection system, contrast management system, or contrast media transfer set approved or cleared for use with this contrast agent in this IBP.
- See drug and device labeling for information on devices indicated for use with this IBP and techniques to help assure safe use.
- The ELUCIREM IBP is to be used only in a room designated to perform radiological procedures that involve administration of a contrast agent.
- Utilize aseptic technique for penetrating the container closure of the IBP and transferring ELUCIREM.
- Penetrate the container closure only one time with a suitable sterile component of the automated contrast injection system, contrast management system, or contrast media transfer set (e.g., transfer spike) approved or cleared for use with this IBP.
- During the entire period of use, ensure that the contents of the ELUCIREM IBP container are in continuous contact with the automated contrast injector system, contrast management system or contrast media transfer set. Do not remove the dispensing set from the IBP container closure to ensure that the protection of the contrast media against any possible contamination.
- Once the ELUCIREM IBP container is punctured, do not remove it from the work area. Store the ELUCIREM IBP at 25° C (77° F); excursions permitted from 15°C to 30°C (59°F to 86°F) [see USP Controlled Room Temperature].
- A maximum use time from initial puncture is 24 hours. Discard any unused ELUCIREM 24 hours after initial puncture of the IBP.
- After the container closure is punctured, if the integrity of IBP and the delivery system cannot be assured through direct continuous supervision, the IBP and all associated disposables for the automated contrast injection system, contrast management system, or contrast media transfer set should be discarded.
- If solidification occurs in the IBP because of exposure to the cold, bring the IBP container of ELUCIREM to room temperature, before use and inspect that the solution is clear, colorless to yellow without any particulate matter and discoloration.

3 DOSAGE FORMS AND STRENGTHS

Injection: ELUCIREM is a clear, colorless to yellow aqueous solution at a concentration of 0.5 mmol/mL of gadopiclenol available as:

Strength | Packaging
- 1.5 mmol/3 mL (0.5 mmol/mL) - 3.75 mmol/7.5 mL (0.5 mmol/mL) - 5 mmol/10 mL (0.5 mmol/mL) - 7.5 mmol/15 mL (0.5 mmol/mL) | Single-dose vials (glass)
- 3.75 mmol/7.5 mL (0.5 mmol/mL) - 5 mmol/10 mL (0.5 mmol/mL) - 7.5 mmol/15 mL (0.5 mmol/mL) | Single-dose prefilled syringes (plastic)
- 15 mmol/30 mL (0.5 mmol/mL) - 25 mmol/50 mL (0.5 mmol/mL) - 50 mmol/100 mL (0.5 mmol/mL) | Pharmacy bulk package (glass)
- 15 mmol/30 mL (0.5 mmol/mL) - 25 mmol/50 mL (0.5 mmol/mL) - 50 mmol/100 mL (0.5 mmol/mL) | Imaging Bulk Package (glass)

4 CONTRAINDICATIONS

ELUCIREM is contraindicated in patients with history of hypersensitivity reactions to ELUCIREM.

5 WARNINGS AND PRECAUTIONS

5.1 Risk Associated with Intrathecal Use

Intrathecal administration of GBCAs can cause serious adverse reactions including death, coma, encephalopathy, and seizures. The safety and effectiveness of ELUCIREM have not been established with intrathecal use. ELUCIREM is not approved for intrathecal use [see Dosage and
Administration (2.1)].

5.2 Nephrogenic Systemic Fibrosis

GBCAs increase the risk for nephrogenic systemic fibrosis (NSF) among patients with impaired elimination of the drugs. Avoid use of ELUCIREM among these patients unless the diagnostic information is essential and not available with non-contrast MRI or other modalities. The GBCA-associated NSF risk appears highest for patients with chronic, severe kidney disease (GFR <30 mL/min/1.73 m^2) as well as patients with acute kidney injury. The risk appears lower for patients with chronic, moderate kidney disease (GFR 30-59 mL/min/1.73 m^2) and little, if any, for patients with chronic, mild kidney disease (GFR 60-89 mL/min/1.73 m^2). NSF may result in fatal or debilitating fibrosis affecting the skin, muscle, and internal organs. Report any diagnosis of NSF following ELUCIREM administration to Guerbet LLC (1-877-729-6679) or FDA (1-800-FDA-1088 or www.fda.gov/medwatch).

Screen patients for acute kidney injury and other conditions that may reduce renal function. Features of acute kidney injury consist of rapid (over hours to days) and usually reversible decrease in kidney function, commonly in the setting of surgery, severe infection, injury or drug-induced kidney toxicity. Serum creatinine levels and estimated GFR may not reliably assess renal function in the setting of acute kidney injury. For patients at risk for chronically reduced renal function (e.g., age >60 years, diabetes mellitus or chronic hypertension), estimate the GFR through laboratory testing.

Among the factors that may increase the risk for NSF are repeated or higher than recommended doses of a GBCA and the degree of renal impairment at the time of exposure. Record the specific GBCA and the dose administered to a patient. For patients at highest risk for NSF, do not exceed the recommended ELUCIREM dose and allow a sufficient period of time for elimination of the drug prior to re-administration. For patients receiving hemodialysis, physicians may consider the prompt initiation of hemodialysis following the administration of a GBCA in order to enhance the contrast agent’s elimination [see Use in Specific Populations (8.6) and Clinical Pharmacology (12.3)]. The usefulness of hemodialysis in the prevention of NSF is unknown.

5.3 Hypersensitivity Reactions

With GBCAs, serious hypersensitivity reactions have occurred. In most cases, initial symptoms occurred within minutes of GBCA administration and resolved with prompt emergency treatment.

- Before ELUCIREM administration, assess all patients for any history of a reaction to contrast media, bronchial asthma and/or allergic disorders. These patients may have an increased risk for a hypersensitivity reaction to ELUCIREM.
- ELUCIREM is contraindicated in patients with history of hypersensitivity reactions to ELUCIREM [see Contraindications (4)].
- Administer ELUCIREM only in situations where trained personnel and therapies are promptly available for the treatment of hypersensitivity reactions, including personnel trained in resuscitation.
- During and following ELUCIREM administration, observe patients for signs and symptoms of hypersensitivity reactions.

5.4 Gadolinium Retention

Gadolinium is retained for months or years in several organs. The highest concentrations (nanomoles per gram of tissue) have been identified in the bone, followed by other organs (e.g. brain, skin, kidney, liver, and spleen). The duration of retention also varies by tissue and is longest in bone. Linear GBCAs cause more retention than macrocyclic GBCAs. At equivalent doses, gadolinium retention varies among the linear agents with gadodiamide causing greater retention than other linear agents such as gadoxetate disodium and gadobenate dimeglumine. Retention is lowest and similar among the macrocyclic GBCAs such as gadoterate meglumine, gadobutrol, gadoteridol, and gadopiclenol.

Consequences of gadolinium retention in the brain have not been established. Pathologic and clinical consequences of GBCA administration and retention in skin and other organs have been established in patients with impaired renal function [see Warnings and Precautions (5.2)]. There are rare reports of pathologic skin changes in patients with normal renal function. Adverse events involving multiple organ systems have been reported in patients with normal renal function without an established causal link to gadolinium.

While clinical consequences of gadolinium retention have not been established in patients with normal renal function, certain patients might be at higher risk. These include patients requiring multiple lifetime doses, pregnant and pediatric patients, and patients with inflammatory conditions. Consider the retention characteristics of the agent when choosing a GBCA for these patients. Minimize repetitive GBCA imaging studies, particularly closely spaced studies, when possible.

5.5 Acute Kidney Injury

In patients with chronically reduced renal function, acute kidney injury requiring dialysis has occurred with the use of GBCAs. The risk of acute kidney injury may increase with increasing dose of the contrast agent. Do not exceed the recommended dose.

5.6 Extravasation and Injection Site Reactions

Injection site reactions such as injection site pain have been reported in the clinical studies with ELUCIREM [see Adverse Reactions (6.1)]. Extravasation during ELUCIREM administration may result in tissue irritation [see Nonclinical Toxicology (13.2)]. Ensure catheter and venous patency before the injection of ELUCIREM.

5.7 Interference with Visualization of Lesions Visible with Non-Contrast MRI

As with any GBCA, ELUCIREM may impair the visualization of lesions seen on non-contrast MRI. Therefore, caution should be exercised when Gadopiclenol MRI scans are interpreted without a companion non-contrast MRI scan.

6 ADVERSE REACTIONS

The following clinically significant adverse reactions are discussed elsewhere in labeling:

- Nephrogenic Systemic Fibrosis [see Warnings and Precautions (5.2)]
- Hypersensitivity Reactions [see Contraindications (4) and Warnings and Precautions (5.3)]

6.1 Clinical Trials Experience

Because clinical trials are conducted under widely varying conditions, adverse reaction rates observed in the clinical trials of a drug cannot be directly compared to rates in the clinical trials of another drug and may not reflect the rates observed in clinical practice.

The safety of ELUCIREM was evaluated in 1,047 patients who received ELUCIREM at doses ranging from 0.025 mmol/kg (one half the recommended dose) to 0.3 mmol/kg (six times the recommended dose). A total of 708 patients received the recommended dose of 0.05 mmol/kg. Among patients who received the recommended dose, the average age was 51 years (range 2 years to 88 years) and 56% were female. The ethnic distribution was 79% White, 10% Asian, 7% American Indian or Alaska native, 2% Black, and 2% patients of other or unspecified ethnic groups.

Overall, approximately 4.7% of subjects receiving the labeled dose reported one or more adverse reactions.

Table 1 lists adverse reactions that occurred in > 0.2% of patients who received 0.05 mmol/kg ELUCIREM.

Table 1. Adverse Reactions Reported in > 0.2% of Patients Receiving ELUCIREM in Clinical Trials
Adverse Reaction | ELUCIREM 0.05 mmol/kg (n=708) (%)
Injection site pain | 0.7
Headache | 0.7
Nausea | 0.4
Injection site warmth | 0.4
Injection site coldness | 0.3
Dizziness | 0.3
Localized swelling | 0.3

Adverse reactions that occurred with a frequency ≤ 0.2% in patients who received 0.05 mmol/kg ELUCIREM included: maculopapular rash, vomiting, worsened renal impairment, feeling hot, pyrexia, oral paresthesia, dysgeusia, diarrhea, pruritus, allergic dermatitis, erythema, injection site paresthesia, Cystatin C increase, and blood creatinine increase.

Adverse Reactions in Pediatric Patients
One study with a single dose of ELUCIREM (0.05 mmol/kg) was conducted in 80 pediatric patients aged 2 years to 17 years, including 60 patients who underwent a central nervous system (CNS) MRI and 20 patients who underwent a body MRI. One adverse reaction (maculopapular rash of moderate severity) in one patient (1.3%) was reported in the CNS cohort.

6.2 Postmarketing Experience

The following additional adverse reactions have been identified during postmarketing use of ELUCIREM or other GBCAs. Because these reactions are reported voluntarily from a population of uncertain size, it is not always possible to reliably estimate their frequency or establish a causal relationship to drug exposure.

Gastrointestinal Disorders: Acute pancreatitis with onset within 48 hours after GBCA administration.

Respiratory, Thoracic and Mediastinal Disorders: Acute respiratory distress syndrome, pulmonary edema.

8 USE IN SPECIFIC POPULATIONS

8.1 Pregnancy

Risk Summary
There are no available data on ELUCIREM use in pregnant women to evaluate for a drug-associated risk of major birth defects, miscarriage or other adverse maternal or fetal outcomes. GBCAs cross the human placenta and result in fetal exposure and gadolinium retention. The available human data on GBCA exposure during pregnancy and adverse fetal outcomes are limited and inconclusive (see Data).

In animal reproduction studies, there were no adverse developmental effects observed in rats or rabbits with intravenous administration of ELUCIREM during organogenesis (see Data). Because of the potential risks of gadolinium to the fetus, use ELUCIREM only if imaging is essential during pregnancy and cannot be delayed.

The estimated background risk of major birth defects and miscarriage for the indicated population(s) are unknown. All pregnancies have a background risk of birth defect, loss, or other adverse outcomes. In the U.S. general population, the estimated background risk of major birth defects and miscarriage in clinically recognized pregnancies is 2% to 4% and 15% to 20% respectively.

Data
Human Data
Contrast enhancement is visualized in the placenta and fetal tissues after maternal GBCA administration.

Cohort studies and case reports on exposure to GBCAs during pregnancy have not reported a clear association between GBCAs and adverse effects in the exposed neonates. However, a retrospective cohort study comparing pregnant women who had a GBCA MRI to pregnant women who did not have an MRI reported a higher occurrence of stillbirths and neonatal deaths in the group receiving GBCA MRI. Limitations of this study include a lack of comparison with non-contrast MRI and lack of information about the maternal indication for MRI. Overall, these data preclude a reliable evaluation of the potential risk of adverse fetal outcomes with the use of GBCAs in pregnancy.

Animal Data
Gadolinium Retention: GBCAs administered to pregnant non-human primates (0.1 mmol/kg on gestational days 85 and 135) result in measurable gadolinium concentration in the offspring in bone, brain, skin, liver, kidney, and spleen for at least 7 months. GBCAs administered to pregnant mice (2 mmol/kg daily on gestational days 16 through 19) result in measurable gadolinium concentrations in the pups in bone, brain, kidney, liver, blood, muscle, and spleen at one-month postnatal age.

Reproductive Toxicology: Animal reproduction studies conducted with gadopiclenol showed some signs of maternal toxicity in rats at 10 mmol/kg and rabbits at 5 mmol/kg (corresponding to 52 times and 57 times the recommended human dose, respectively). This maternal toxicity was characterized in both species by swelling, decreased activity, and lower gestation weight gain and food consumption.

No effect on embryo-fetal development was observed in rats at 10 mmol/kg (corresponding to 52 times the recommended human dose). In rabbits, a lower mean fetal body weight was observed at 5 mmol/kg (corresponding to 57 times the recommended human dose) and this was attributed as a consequence of the lower gestation weight gain.

8.2 Lactation

Risk Summary
There are no data on the presence of gadopiclenol in human milk, the effects on the breastfed infant, or the effects on milk production. However, published lactation data on other GBCAs indicate that 0.01% to 0.04% of the maternal gadolinium dose is excreted in breast milk. Additionally, there is limited GBCA gastrointestinal absorption in the breast-fed infant. Gadopiclenol is present in rat milk. When a drug is present in animal milk, it is likely that the drug will be present in human milk (see Data). The developmental and health benefits of breastfeeding should be considered along with the mother’s clinical need for ELUCIREM and any potential adverse effects on the breastfed infant from ELUCIREM or from the underlying maternal condition.

Data
In lactating rats receiving single intravenous injection of [^153Gd]-gadopiclenol, 0.3% and 0.2% of the total administered radioactivity was transferred to the pups via maternal milk at 6 hours and 24 hours after administration, respectively. Furthermore, in nursing rat pups, oral absorption of gadopiclenol was 3.6%.

8.4 Pediatric Use

The safety and effectiveness of ELUCIREM for use with MRI to detect and visualize lesions with abnormal vascularity in the CNS (brain, spine, and associated tissues), and the body (head and neck, thorax, abdomen, pelvis, and musculoskeletal system) have been established in pediatric patients aged 2 years and older.

Use of ELUCIREM in this age group is supported by evidence from adequate and well-controlled studies in adults with additional pharmacokinetic and safety data from an open-label, uncontrolled, multicenter, single dose study of ELUCIREM (0.05 mmol/kg) in 80 pediatric patients aged 2 to 17 years. The 80 patients consisted of 60 patients who underwent a CNS MRI and 20 patients who underwent a body MRI [see Adverse Reactions (6.1) and Clinical Pharmacology (12.3)].

The safety and effectiveness of ELUCIREM have not been established in pediatric patients younger than 2 years of age.

8.5 Geriatric Use

Of the total number of ELUCIREM-treated patients in clinical studies, 270 (26%) patients were 65 years of age and over, while 62 (6%) patients were 75 years of age and over. No overall differences in safety or efficacy were observed between these subjects and younger subjects.

This drug is known to be substantially excreted by the kidney, and the risk of adverse reactions to this drug may be greater in patients with impaired renal function. Because elderly patients are more likely to have decreased renal function, it may be useful to monitor renal function.

8.6 Renal impairment

In patients with renal impairment, the exposure of gadopiclenol is increased compared to patients with normal renal function. This may increase the risk of adverse reactions such as nephrogenic systemic fibrosis (NSF). Avoid use of GBCAs among these patients unless the diagnostic information is essential and not available with non-contrast MRI or other modalities. No dose adjustment of ELUCIREM is recommended for patients with renal impairment. ELUCIREM can be removed from the body by hemodialysis [see Warnings and Precautions (5.2, 5.4, 5.5) and Clinical Pharmacology (12.3)].

10 OVERDOSAGE

Among subjects who received a single 0.3 mmol/kg intravenous dose of gadopiclenol (6 times the recommended dose of ELUCIREM), headache and nausea were the most frequently reported adverse reactions. Gadopiclenol can be removed from the body by hemodialysis [see Clinical Pharmacology (12.3)].

11 DESCRIPTION

ELUCIREM is a gadolinium-based contrast agent, which contains gadopiclenol, a paramagnetic macrocyclic non-ionic complex of gadolinium.

The chemical name for gadopiclenol is rac-[(2R,2'Ξ,2''Ξ)-2,2',2''-(3,6,9-triaza-κ^3N^3,N^6,N^9-1(2,6)-pyridina-κN^1-cyclodecaphane-3,6,9-triyl)tris(5-{[(2Ξ)-2,3-dihydroxypropyl]amino}-5-oxopentanoato-κ^3O^1,O^1',O^1'')(3−)]gadolinium with a molecular weight of 970.11 g/mol and a molecular formula of 970.11 g/mol and a molecular formula of C35 H54 GdN7 O15

ELUCIREM is a sterile, nonpyrogenic, clear, colorless to yellow aqueous solution for intravenous use.

Each mL contains 485.1 mg of gadopiclenol (equivalent to 0.5 mmol of gadopiclenol and 78.6 mg of gadolinium) and the following inactive ingredients: 0.404 mg tetraxetan, 1.211 mg trometamol, hydrochloric acid and/or sodium hydroxide (for pH adjustment, if needed), and water for injection.

The main physicochemical properties of ELUCIREM are provided in Table 2.

Table 2. Physicochemical properties of ELUCIREM
Parameter | Value
Density at 20°C | 1.211 g/cm^3
Mean viscosity at 20°C | 12.6 mPa.s
Mean viscosity at 37°C | 7.6 mPa.s
Osmolality at 37°C | 850 mOsm/kg water
pH | 7.0 – 7.8

12 CLINICAL PHARMACOLOGY

12.1 Mechanism of Action

Gadopiclenol is a paramagnetic molecule (macrocyclic non-ionic complex of gadolinium) that develops a magnetic moment when placed in a magnetic field. The magnetic moment alters the relaxation rates of water protons in its vicinity in the body, leading to an increase in signal intensity (brightness) of tissues.

12.2 Pharmacodynamics

In MRI, visualization of normal and pathological tissue depends in part on variations in the radiofrequency signal intensity that occur with:

- differences in proton density
- differences of the spin-lattice or longitudinal relaxation times (T1)
- differences in the spin-spin or transverse relaxation time (T2).

When placed in a magnetic field (patient in MRI machine), gadopiclenol shortens the T1 and T2 relaxation times in targeted tissues. The extent to which a contrast agent can affect the relaxation rate of tissue water (1/T1 or 1/T2) is termed relaxivity (r1 or r2).
The relaxivity of GBCAs is presented in Table 3.

Table 3. Relaxivity (r1) of GBCAs in Human Plasma/Serum at 1.5 T and 37°C
Gadolinium-Chelate | r1 (L.mmol^-1.s^-1)
Gadobenic acid | 6.3
Gadobutrol | 5.2
Gadodiamide | 4.3
Gadopentetic acid | 4.1
Gadopiclenol | 12.8
Gadoteric acid | 3.6
Gadoteridol | 4.1
Gadoxetic acid | 6.9

Cardiac Electrophysiology
At 6 times the recommended dosage in adult patients, gadopiclenol does not prolong the QT interval to any clinically relevant extent.

12.3 Pharmacokinetics

The Cmax and AUCinf of gadopiclenol increased proportionally over a dosage range from 0.025 mmol/kg to 0.3 mmol/kg (0.5 times to 6 times the recommended dosage). At the recommended dose, the mean (CV%) Cmax and AUCinf were 525 (13%) µg/mL and 569 (18%) µg·h/mL, respectively.

Distribution
After intravenous administration of ELUCIREM, gadopiclenol is distributed in the extracellular fluids.

The mean (CV%) volume of distribution of gadopiclenol at steady state is 13 (13%) L.

Protein binding of gadopiclenol is ≤ 1.8% at clinically relevant concentrations.

Following GBCA administration, gadolinium is present for months or years in brain, bone, skin, and other organs [see Warnings and Precautions (5.4)]. It is unknown whether the recommended dose of ELUCIREM results in similar or different levels of gadolinium retention relative to those of other approved macrocyclic GBCAs at their recommended doses.

Elimination

The mean (CV%) elimination half-life (t1/2) of gadopiclenol is 1.5 (14%) hour.

The mean (CV%) total body clearance (CL) and renal clearance (CLr) of gadopiclenol are 100 (9.5%) mL/min and 81 (35%) mL/min, respectively.

Metabolism
Gadopiclenol is not metabolized.

Excretion
Gadopiclenol is mainly eliminated through the kidneys by glomerular filtration. Approximately 98% of the dose was recovered in urine within 48 hours after administration.

Specific Populations

No clinically significant differences in the pharmacokinetics of gadopiclenol were observed based on sex.

Pediatric Patients
The pharmacokinetics of gadopiclenol for pediatric patients (2 to 17 years of age) were within range to those of adults (> 18 years of age) [see Dosage and Administration (2.1)].

The pharmacokinetic parameters (median [range]) of gadopiclenol in pediatric patients are presented in Table 4.

Table 4. Pharmacokinetics Parameters (Median [Range])a According to Age Classes
 | 2-6 years | 7-11 years | 12-17 years | >18 years
Cl (L/h/kg) | 0.12 [0.05; 0.28] | 0.10 [0.04; 0.24] | 0.08 [0.04; 0.20] | 0.08 [0.05; 0.14]
t1/2 (h) | 1.29 [0.69; 3.38] | 1.48 [0.83; 3.20] | 1.77 [1.00; 3.57] | 1.82 [0.93; 3.68]
AUCinf (ng.h/L) | 403 [169; 964] | 478 [183; 1077] | 582 [267; 1291] | 590 [353; 937]
C20 (µg/mL) | 236 [136; 387] | 260 [151; 401] | 286 [155; 441] | 296 [166; 485]

aAt the recommended dosage

Patients with Renal Impairment

The pharmacokinetic parameters (mean (%CV)) of gadopiclenol in patients with renal impairment are presented in Table 5.

Table 5. Effect of Renal Impairment on the Pharmacokinetics of Gadopiclenola,b
 | Normal (eGFR ≥ 90 mL/min) | Mild (eGFR 60 to < 90 mL/min) | Moderate (eGFR 30 to < 60 mL/min) | Severe (eGFR 15 to < 30 mL/min)
AUCinf (µg·h/mL) | 1113 (24%) | 1711 (31%) | 2759 (28%) | 9671 (18%)
CLr (mL/min) | 96 (10%) | 76 (23%) | 44 (25%) | 14 (26%)
t1/2 (h) | 1.9 | 3.3 | 3.8 | 11.7

a Following administration of a single gadopiclenol 0.1 mmol/kg dose (2 times the recommended dosage).
b eGFR: estimate of GFR based on an estimation equation and expressed in mL/min. To convert mL/min/1.73 m^2 to mL/min, multiply by the individual’s BSA and divide by 1.73.

In patients with mild or moderate renal impairment, more than 90% of the administered ELUCIREM was recovered in urine within 48 hours. In patients with severely impaired renal function about 84% of the administered ELUCIREM was recovered in urine within 5 days.

In patients with eGFR < 15 mL/min, hemodialysis effectively removed gadopiclenol from plasma as the percentage of decrease in blood concentrations was 95 to 98% at the end of the first hemodialysis session and 100% after the third hemodialysis session [see Warnings and Precautions (5.2), Use in Specific Populations (8.6)].

13 NONCLINICAL TOXICOLOGY

13.1 Carcinogenesis, Mutagenesis, Impairment of Fertility

Carcinogenesis
No carcinogenicity studies of gadopiclenol were performed.

Mutagenesis
Gadopiclenol did not demonstrate mutagenic potential in in vitro bacterial reverse mutation assays (Ames test), in an in vitro chromosome aberration assay in Chinese hamster ovary cells nor in an in vivo rat micronucleus assay.

Impairment of Fertility
Gadopiclenol had no effect on fertility and general reproductive performance of male and female rats when given at dose up to 10 mmol/kg (corresponding to 62 times the recommended human dose).

13.2 Animal Toxicology

Local intolerance reactions, including slight to moderate erythema and edema, were observed after perivenous injection in rabbits suggesting the possibility of local irritation if the contrast medium leaks around the veins in a clinical setting [see Warnings and Precautions (5.6)].

14 CLINICAL STUDIES

14.1 Overview of Clinical Studies

The safety and effectiveness of ELUCIREM for lesion visualization were evaluated in two prospective, double blind, randomized, crossover clinical studies. Study 1 (NCT03996447) was performed in adults with known or highly suspected CNS lesions with focal areas of disruption of the blood-brain barrier. Study 2 (NCT03986138) was performed in adults with suspected enhancing abnormalities in at least one body region among the head and neck, thorax, abdomen, pelvis, and musculoskeletal system.

In each study, patients received both ELUCIREM 0.05 mmol/kg and gadobutrol 0.1 mmol/kg (as an active comparator) in random order separated by 2 days to 14 days. Magnetic resonance imaging was performed before and after administration of each contrast agent.

Pre-contrast and paired (consisting of both pre-contrast and post-contrast images for the same drug) image sets were independently evaluated by three central readers who were blinded to identity of the contrast agent. Readers scored up to three lesions per patient for border delineation, internal morphology, and contrast enhancement, each on a scale from 1 to 4. The total number of lesions was also reported. An additional independent central reader performed lesion tracking to allow matching of lesions between pre-contrast and paired images.

The analysis compared the patient-level average score for matching lesions for each visualization parameter between pre-contrast and paired image sets.

14.2 Visualization of CNS Lesions

Study 1 included 256 patients with known or highly suspected CNS lesion(s). Among the enrolled patients, 239 had assessable pre-contrast and paired images with at least one matching lesion for at least one reader. These patients had a mean age of 57 years (range: 18 years to 84 years), 52% were female, and 83% were White.

All three blinded readers’ evaluations of paired pre-contrast plus post-contrast images and pre-contrast images alone for all lesion visualization criteria, the pre-specified co-primary efficacy endpoints, are presented in Table 6.

Table 6. Patient-Level CNS Lesion Visualization Scores by Reader, Paired vs. Pre-contrast in Patients Receiving ELUCIREM 0.05 mmol/kg Intravenously
 | n | LS Mean (SE) |  |  | 95% CI Difference
 | n | Paired | Pre-contrast | Difference* | 95% CI Difference
Border delineation
Reader 1 | 227 | 3.90 (0.02) | 2.08 (0.02) | 1.82 (0.03) | (1.76, 1.88)
Reader 2 | 229 | 3.64 (0.04) | 1.74 (0.04) | 1.90 (0.05) | (1.81, 2.00)
Reader 3 | 202 | 3.97 (0.03) | 2.61 (0.03) | 1.36 (0.04) | (1.29, 1.44)
Internal morphology
Reader 1 | 227 | 3.92 (0.03) | 1.66 (0.03) | 2.26 (0.03) | (2.20, 2.33)
Reader 2 | 229 | 3.65 (0.03) | 1.88 (0.03) | 1.77 (0.04) | (1.69, 1.85)
Reader 3 | 202 | 3.97 (0.04) | 2.01 (0.04) | 1.96 (0.05) | (1.85, 2.06)
Degree of contrast enhancement
Reader 1 | 227 | 3.77 (0.03) | 1.00 (0.03) | 2.77 (0.04) | (2.69, 2.85)
Reader 2 | 229 | 3.58 (0.03) | 1.00 (0.03) | 2.58 (0.05) | (2.49, 2.67)
Reader 3 | 202 | 3.90 (0.02) | 1.00 (0.02) | 2.90 (0.03) | (2.84, 2.95)

LS: Least Squares; SE: Standard Error; CI: Confidence Interval.
Only matching lesions are considered. The mixed models based on the full analysis set (N=239) include lesion visualization factor as dependent variable, MRI modality (Precontrast and Paired MRI) as fixed factors, and patient as a random factor.
*p<0.0001 for all rows

Gadopiclenol lesion visualization scores and number of lesions identified per patient were similar to those for gadobutrol.

14.3 Visualization of Body Lesions

Study 2 included 304 patients presenting with known or suspected enhancing abnormality(ies) and/or lesion(s) in at least one region among the head and neck, musculoskeletal system including extremities, and body including thorax, abdomen, and pelvis. Among the enrolled patients, 278 had assessable pre-contrast and paired images with at least one matching lesion for at least one reader. These patients had a mean age of 57 years (range: 21 years to 86 years), 59% were female, and 71% were White.

Three readers assessed images of the head and neck, three other readers assessed images of the musculoskeletal system, and another three readers assessed other areas collectively referred to as the body (thorax, abdomen, and pelvis). Lesion visualization scores by reader in each anatomic region at patient-level as supportive analyses are summarized in Table 7.

Table 7. Patient-Level Body Lesion Visualization Scores by Reader and Anatomic Region, Paired vs. Pre-contrast in Patients Receiving ELUCIREM 0.05 mmol/kg Intravenously

 | n | LS Mean (SE) |  |  | 95% CI; difference
 | n | Paired | Pre-contrast | Difference | 95% CI; difference
Head & Neck
Border delineation
Reader 1 | 15 | 3.71 (0.10) | 2.13 (0.10) | 1.58 (0.14) | (1.30, 1.86)
Reader 2 | 19 | 3.53 (0.18) | 2.11 (0.18) | 1.42 (0.18) | (1.06, 1.78)
Reader 3 | 13 | 3.92 (0.13) | 2.85 (0.13) | 1.08 (0.13) | (0.82, 1.33)
Internal morphology
Reader 1 | 15 | 3.80 (0.07) | 1.87 (0.07) | 1.93 (0.10) | (1.74, 2.12)
Reader 2 | 19 | 3.74 (0.14) | 2.05 (0.14) | 1.68 (0.16) | (1.37, 2.00)
Reader 3 | 13 | 3.92 (0.12) | 2.54 (0.12) | 1.38 (0.14) | (1.10, 1.67)
Degree of contrast enhancement
Reader 1 | 15 | 3.60 (0.11) | 1.00 (0.11) | 2.60 (0.16) | (2.29, 2.91)
Reader 2 | 19 | 3.68 (0.16) | 1.00 (0.16) | 2.68 (0.22) | (2.22, 3.15)
Reader 3 | 13 | 3.92 (0.11) | 1.00 (0.11) | 2.92 (0.15) | (2.61, 3.24)
Musculoskeletal system (including extremities)
Border delineation
Reader 1 | 17 | 3.00 (0.10) | 2.06 (0.10) | 0.94 (0.13) | (0.68, 1.20)
Reader 2 | 17 | 2.68 (0.20) | 2.44 (0.20) | 0.24 (0.19) | (-0.15, 0.62)
Reader 3 | 21 | 2.81 (0.10) | 2.05 (0.10) | 0.76 (0.10) | (0.56, 0.96)
Internal morphology
Reader 1 | 17 | 3.00 (0.07) | 2.00 (0.07) | 1.00 (0.09) | (0.82, 1.18)
Reader 2 | 17 | 3.94 (0.15) | 2.35 (0.15) | 1.59 (0.17) | (1.25, 1.92)
Reader 3 | 21 | 2.90 (0.09) | 2.05 (0.09) | 0.86 (0.11) | (0.64, 1.08)
Degree of contrast enhancement
Reader 1 | 17 | 2.82 (0.10) | 1.00 (0.10) | 1.82 (0.15) | (1.53, 2.12)
Reader 2 | 17 | 3.33 (0.17) | 1.00 (0.17) | 2.33 (0.24) | (1.847, 2.82)
Reader 3 | 21 | 3.06 (0.08) | 1.00 (0.08) | 2.06 (0.12) | (1.82, 2.31)
Body (thorax, abdomen, pelvis)
Border delineation
Reader 1 | 219 | 3.86 (0.03) | 2.28 (0.03) | 1.57 (0.04) | (1.50, 1.64)
Reader 2 | 194 | 3.54 (0.06) | 3.15 (0.06) | 0.40 (0.06) | (0.29, 0.51)
Reader 3 | 228 | 3.53 (0.03) | 1.69 (0.03) | 1.84 (0.03) | (1.78, 1.90)
Internal morphology
Reader 1 | 219 | 3.86 (0.02) | 2.00 (0.02) | 1.87 (0.03) | (1.82, 1.92)
Reader 2 | 194 | 3.74 (0.05) | 3.41 (0.05) | 0.33 (0.05) | (0.23, 0.43)
Reader 3 | 228 | 3.78 (0.03) | 1.60 (0.03) | 2.17 (0.03) | (2.11, 2.24)
Degree of contrast enhancement
Reader 1 | 219 | 3.71 (0.03) | 1.00 (0.03) | 2.71 (0.04) | (2.63, 2.79)
Reader 2 | 194 | 2.69 (0.05) | 1.00 (0.05) | 1.69 (0.07) | (1.54, 1.83)
Reader 3 | 228 | 3.33 (0.03) | 1.00 (0.03) | 2.33 (0.44) | (2.25, 2.40)

LS: Least Squares; SE: Standard Error; CI: Confidence Interval.
Only matching lesions are considered. The mixed models based on the full analysis set (N=278) include lesion visualization factor as a dependent variable, patient as a random factor, and MRI modality (Pre-contrast and Paired MRI), body regions, and MRI body regions as fixed factors.

Gadopiclenol lesion visualization scores and number of lesions identified per patient were similar to those for gadobutrol.

16 HOW SUPPLIED/STORAGE AND HANDLING

HOW SUPPLIED
ELUCIREM is a clear, colorless to yellow aqueous solution supplied in the following presentations:

Strength | Sale Unit | NDC
Single-Dose Vial (glass)
1.5 mmol/3 mL (0.5 mmol/mL) | Carton of 1 | 67684-4230-1
1.5 mmol/3 mL (0.5 mmol/mL) | Carton of 10 | 67684-4230-2
3.75 mmol/7.5 mL (0.5 mmol/mL) | Carton of 1 | 67684-4231-1
3.75 mmol/7.5 mL (0.5 mmol/mL) | Carton of 10 | 67684-4231-2
5 mmol/10 mL (0.5 mmol/mL) | Carton of 1 | 67684-4232-1
5 mmol/10 mL (0.5 mmol/mL) | Carton of 10 | 67684-4232-2
7.5 mmol/15 mL (0.5 mmol/mL) | Carton of 1 | 67684-4233-1
7.5 mmol/15 mL (0.5 mmol/mL) | Carton of 10 | 67684-4233-2
Single-Dose Prefilled Syringe (plastic)
3.75 mmol/7.5 mL (0.5 mmol/mL) | Carton of 1 | 67684-4240-1
3.75 mmol/7.5 mL (0.5 mmol/mL) | Carton of 10 | 67684-4240-2
5 mmol/10 mL (0.5 mmol/mL) | Carton of 1 | 67684-4241-1
5 mmol/10 mL (0.5 mmol/mL) | Carton of 10 | 67684-4241-2
7.5 mmol/15 mL (0.5 mmol/mL) | Carton of 1 | 67684-4242-1
7.5 mmol/15 mL (0.5 mmol/mL) | Carton of 10 | 67684-4242-2
Pharmacy Bulk Package (glass)
15 mmol/30 mL (0.5 mmol/mL) | Carton of 1 | 67684-4250-1
15 mmol/30 mL (0.5 mmol/mL) | Carton of 25 | 67684-4250-2
25 mmol/50 mL (0.5 mmol/mL) | Carton of 1 | 67684-4250-3
25 mmol/50 mL (0.5 mmol/mL) | Carton of 25 | 67684-4250-4
50 mmol/100 mL (0.5 mmol/mL) | Carton of 1 | 67684-4250-5
50 mmol/100 mL (0.5 mmol/mL) | Carton of 6 | 67684-4250-6
50 mmol/100 mL (0.5 mmol/mL) | Carton of 12 | 67684-4250-7
Imaging Bulk Package (glass)
15 mmol/30 mL (0.5 mmol/mL) | Carton of 1 | 67684-4251-1
15 mmol/30 mL (0.5 mmol/mL) | Carton of 25 | 67684-4251-2
25 mmol/50 mL (0.5 mmol/mL) | Carton of 1 | 67684-4251-3
25 mmol/50 mL (0.5 mmol/mL) | Carton of 25 | 67684-4251-4
50 mmol/100 mL (0.5 mmol/mL) | Carton of 1 | 67684-4251-5
50 mmol/100 mL (0.5 mmol/mL) | Carton of 6 | 67684-4251-6
50 mmol/100 mL (0.5 mmol/mL) | Carton of 12 | 67684-4251-7

Storage and Handling
Store at 25°C (77°F); excursions permitted from 15°C to 30°C (59°F to 86°F) [see USP, Controlled Room Temperature].

Do not freeze Pre-filled syringes.

17 PATIENT COUNSELING INFORMATION

Advise the patient to read the FDA-approved patient labeling (Medication Guide).

Nephrogenic Systemic Fibrosis

Inform the patient that ELUCIREM may increase the risk for NSF among patients with impaired elimination of the drugs and that NSF may result in fatal or debilitating fibrosis affecting the skin, muscle and internal organs.

Instruct the patients to contact their physician if they develop signs or symptoms of NSF following ELUCIREM administration, such as burning, itching, swelling, scaling, hardening and tightening of the skin; red or dark patches on the skin; stiffness in joints with trouble moving, bending or straightening the arms, hands, legs or feet; pain in the hip bones or ribs; or muscle weakness [see Warnings and Precautions (5.2)].

Gadolinium Retention

Advise patients that gadolinium is retained for months or years in brain, bone, skin, and other organs following ELUCIREM administration even in patients with normal renal function. The clinical consequences of retention are unknown. Retention depends on multiple factors and is greater following administration of linear GBCAs than following administration of macrocyclic GBCAs [see Warnings and Precautions (5.4)].

Injection Site Reactions

Inform the patient that ELUCIREM may cause reactions along the venous injection site, such as mild and transient burning or pain or feeling of warmth or coldness at the injection site [see Warnings and Precautions (5.6)].

Pregnancy

Advise pregnant women of the potential risk of fetal exposure to ELUCIREM [see Use in Specific Populations (8.1)].

Vials and pre-filled syringes manufactured by Liebel-Flarsheim Company LLC,
8800 Durant Road, Raleigh, North Carolina (NC) 27616-3104, USA

Vials manufactured by BIPSO GmbH
Robert-Gerwig-Strasse 4, Singen (Hohentwiel) 78224, Germany

Distributed by
Guerbet LLC
214 Carnegie Center, Suite 300, Princeton, NJ 08540, USA

MEDICATION GUIDE
ELUCIREMTM (ah LOOS er em)
(gadopiclenol)
injection, for intravenous use

What is the most important information I should know about ELUCIREM?

- GBCAs like ELUCIREM may cause serious side effects including death, coma, encephalopathy, and seizures when it is given intrathecally (injection given into the spinal canal). It is not known if ELUCIREM is safe and effective with intrathecal use. ELUCIREM is not approved for this use.
- ELUCIREM contains a metal called gadolinium. Small amounts of gadolinium can stay in your body including the brain, bones, skin and other parts of your body for a long time (several months to years).
- It is not known how gadolinium may affect you, but so far, studies have not found harmful effects in patients with normal kidneys.
- Rarely patients have reported pains, tiredness, and skin, muscle or bone ailments for a long time, but these symptoms have not been directly linked to gadolinium.
- There are different GBCAs that can be used for your MRI exam. The amount of gadolinium that stays in the body is different for different gadolinium medicines. Gadolinium stays in the body more after gadodiamide than after gadoxetate disodium or gadobenate dimeglumine. Gadolinium stays in the body the least after, gadoterate meglumine, gadobutrol, gadoteridol, and gadopiclenol.
- People who get many doses of gadolinium medicines, women who are pregnant and young children may be at increased risk from gadolinium staying in the body.
- Some people with kidney problems who get gadolinium medicines can develop a condition with severe thickening of the skin, muscles and other organs in the body (nephrogenic systemic fibrosis). Your healthcare provider should screen you to see how well your kidneys are working before you receive ELUCIREM.

What is ELUCIREM?

- ELUCIREM is a prescription medicine called a gadolinium-based contrast agent (GBCA). ELUCIREM, like other GBCAs, is injected into your vein and used with a magnetic resonance imaging (MRI) scanner.
- An MRI exam with a GBCA, including ELUCIREM, helps your healthcare provider to see problems better than an MRI exam without a GBCA.
- Your healthcare provider has reviewed your medical records and has determined that you would benefit from using a GBCA with your MRI exam.

Do not receive ELUCIREM if you have had a severe allergic reaction to ELUCIREM.

Before receiving ELUCIREM, tell your healthcare provider about all your medical conditions, including if you:

- have had any MRI procedures in the past where you received a GBCA. Your healthcare provider may ask you for more information including the dates of these MRI procedures.
- are pregnant or plan to become pregnant. It is not known if ELUCIREM can harm your unborn baby. Talk to your healthcare provider about the possible risks to an unborn baby if a GBCA such as ELUCIREM is received during pregnancy.
- have kidney problems, diabetes, or high blood pressure.
- have had an allergic reaction to dyes (contrast agents) including GBCAs.

What are possible side effects of ELUCIREM?

- See “What is the most important information I should know about ELUCIREM?”
- Allergic reactions. ELUCIREM can cause allergic reactions that can sometimes be serious. Your healthcare provider will monitor you closely for symptoms of an allergic reaction.

The most common side effects of ELUCIREM include: injection site pain, headache, nausea, injection site coldness, injection site warmth, dizziness, and localized swelling.
These are not all the possible side effects of ELUCIREM.
Call your doctor for medical advice about side effects. You may report side effects to FDA at 1-800-FDA-1088.

General information about the safe and effective uses of ELUCIREM.
Medicines are sometimes prescribed for purposes other than those listed in a Medication Guide. You can ask your healthcare provider for information about ELUCIREM that is written for health professionals.

What are the ingredients in ELUCIREM?
Active ingredient: gadopiclenol
Inactive ingredients: tetraxetan; trometamol; hydrochloric acid or sodium hydroxide for pH adjustment; and water for injection
Manufactured by: Vials and pre-filled syringes manufactured by Liebel-Flarsheim Company LLC, 8800 Durant Road, Raleigh, North Carolina (NC) 27616-3104, USA
Vials manufactured by BIPSO GmbH Robert-Gerwig-Strasse 4, Singen (Hohentwiel) 78224, Germany
Distributed by: Guerbet LLC, 214 Carnegie Center, Suite 300, Princeton, New Jersey 08540, USA
For more information, go to www.guerbet-us.com or call 1-877-729-6679.

This Medication Guide has been approved by the U.S. Food and Drug Administration. Revised: 12/2025

PACKAGE LABEL

Single-Dose Vial (glass)

1.5 mmol/3 mL (0.5 mmol/mL)

3.75 mmol/7.5 mL (0.5 mmol/mL)

5 mmol/10 mL (0.5 mmol/mL)

7.5 mmol/15 mL (0.5 mmol/mL)

PACKAGE LABEL

Single-Dose Prefilled Syringe (plastic)

3.75 mmol/7.5 mL (0.5 mmol/mL)

5 mmol/10 mL (0.5 mmol/mL)

7.5 mmol/15 mL (0.5 mmol/mL)

Pharmacy Bulk Package (glass)

15 mmol/30 mL (0.5 mmol/mL)

25 mmol/50 mL (0.5 mmol/mL)

50 mmol/100 mL (0.05 mmol/mL)

Imaging Bulk Package (glass)

15 mmol/30 mL (0.5 mmol/mL)

25 mmol/50 mL (0.5 mmol/mL)

50 mmol/100 mL (0.05 mmol/mL)